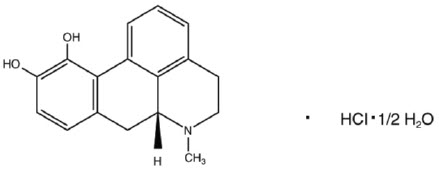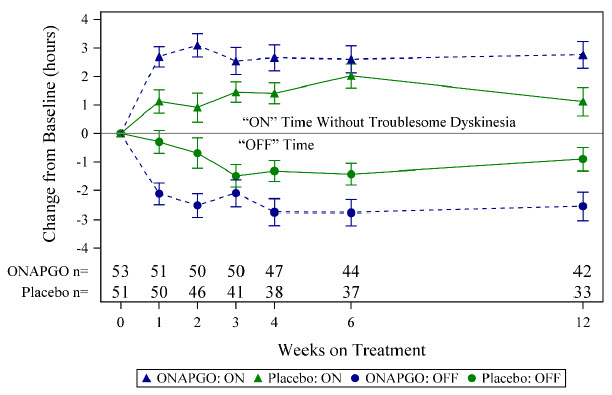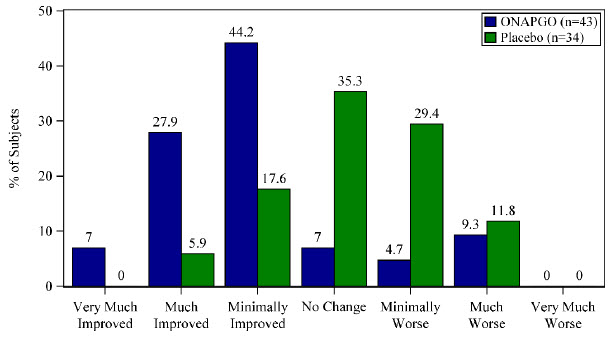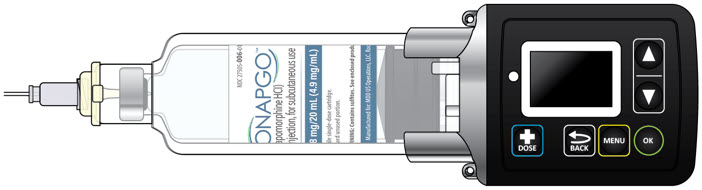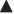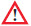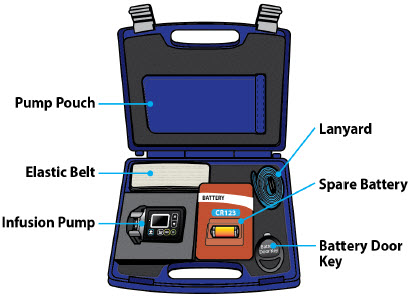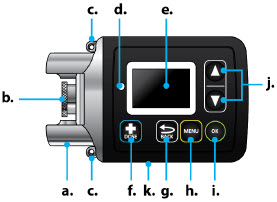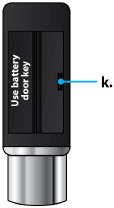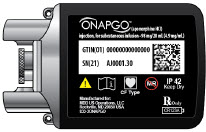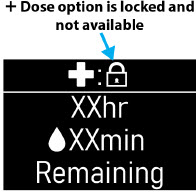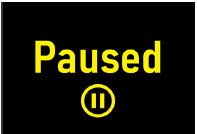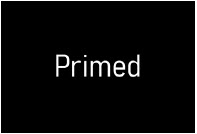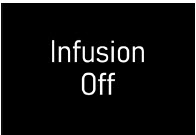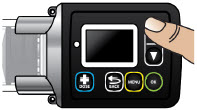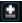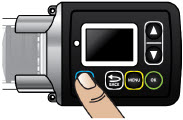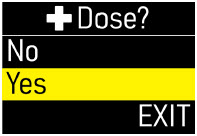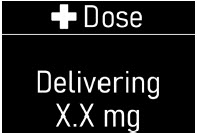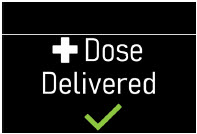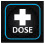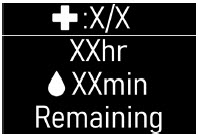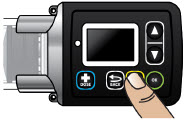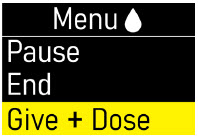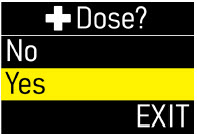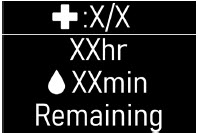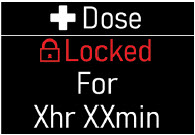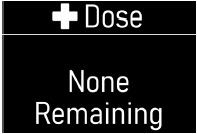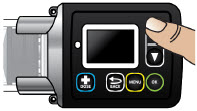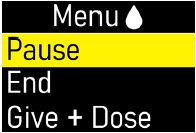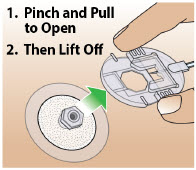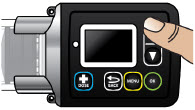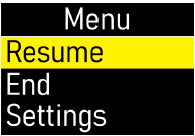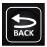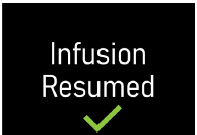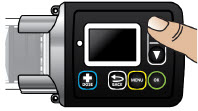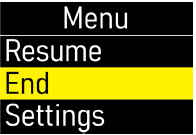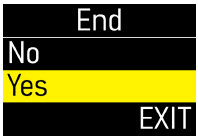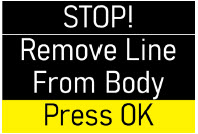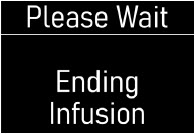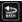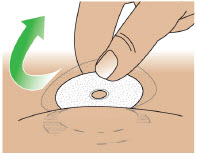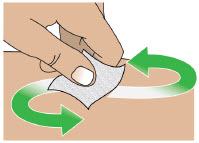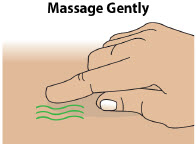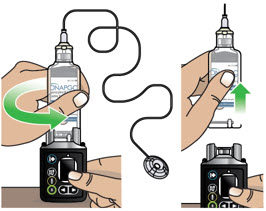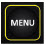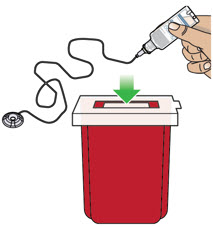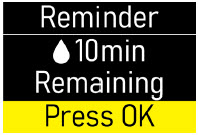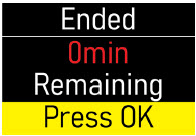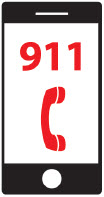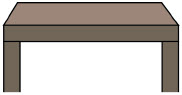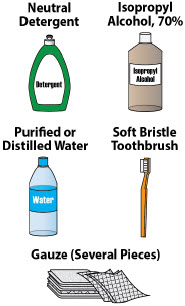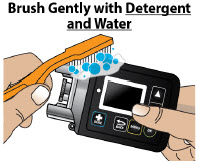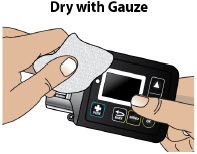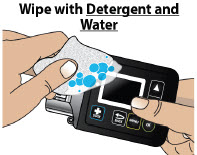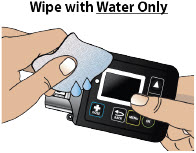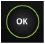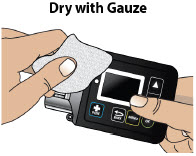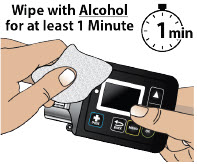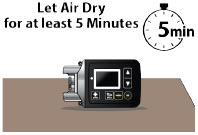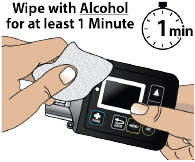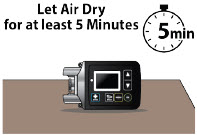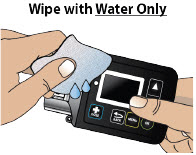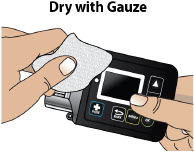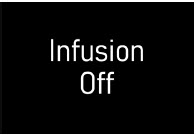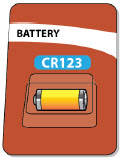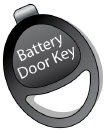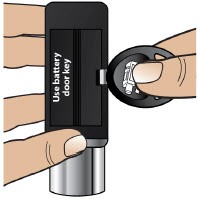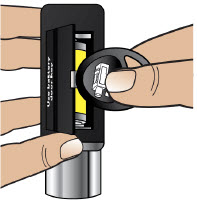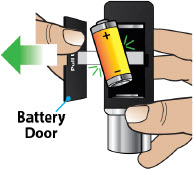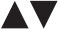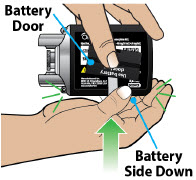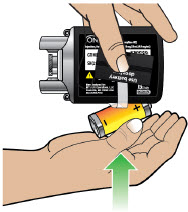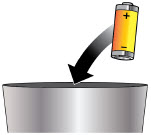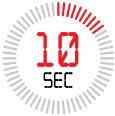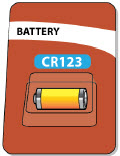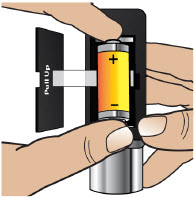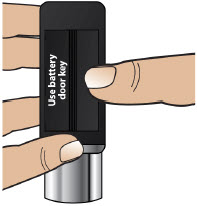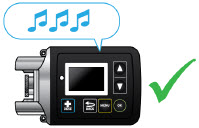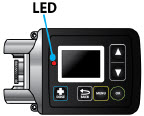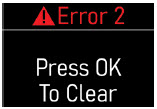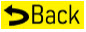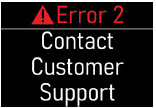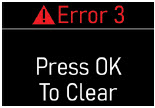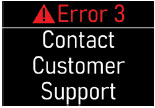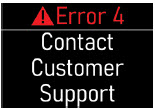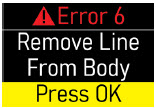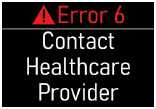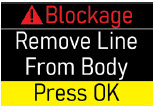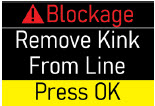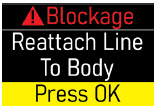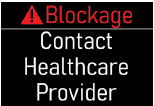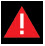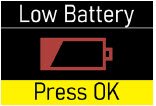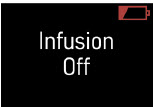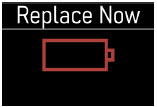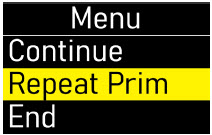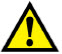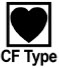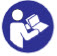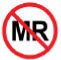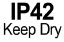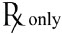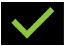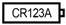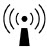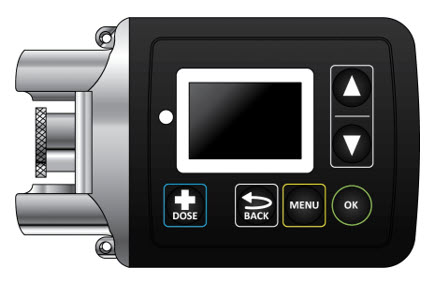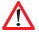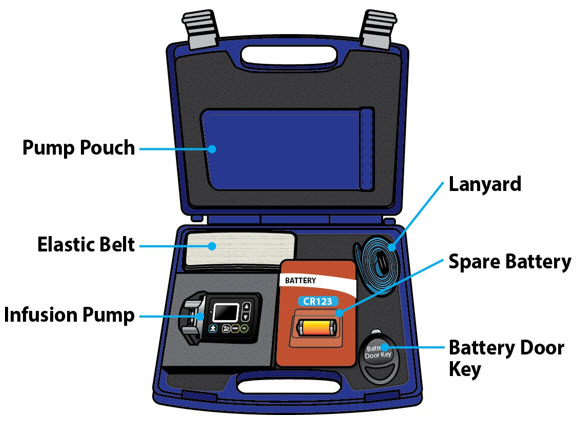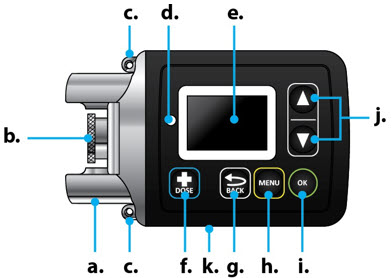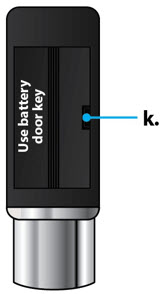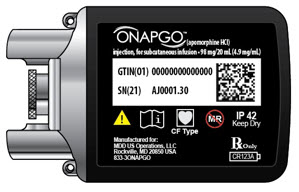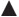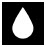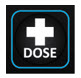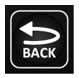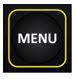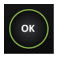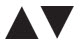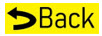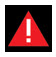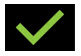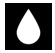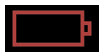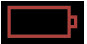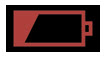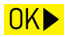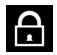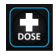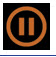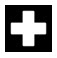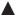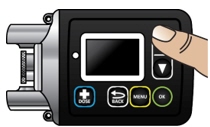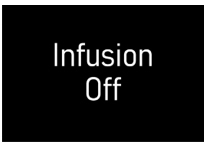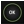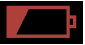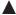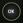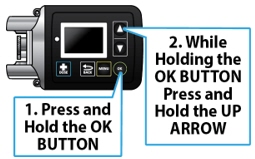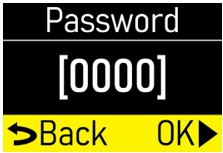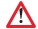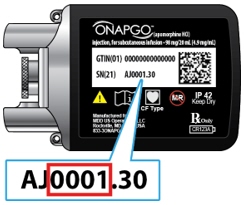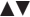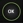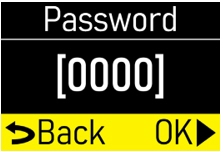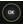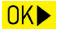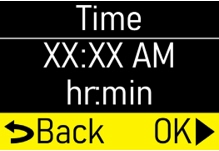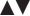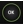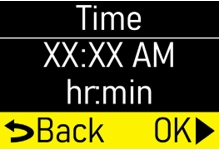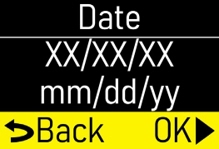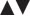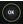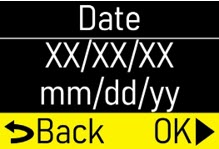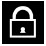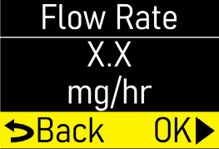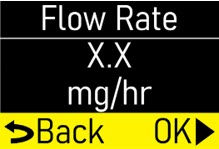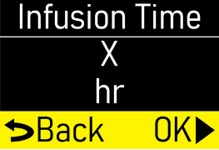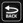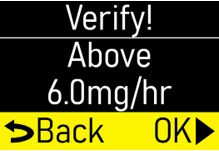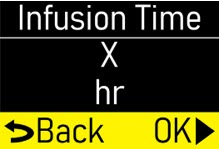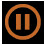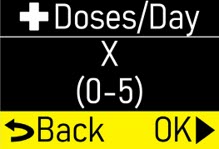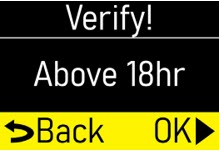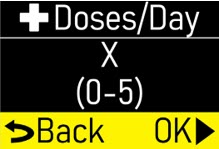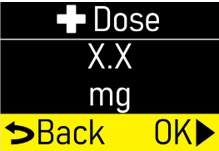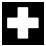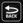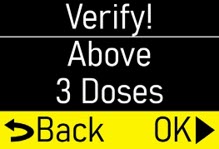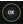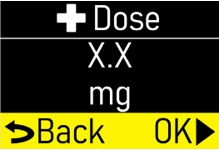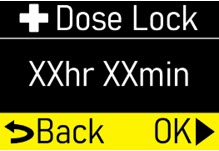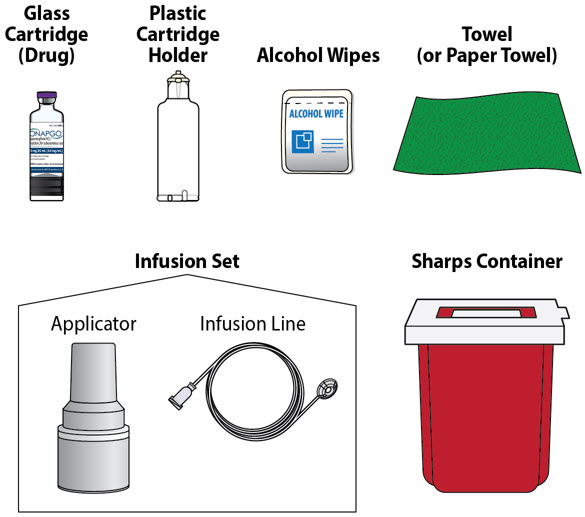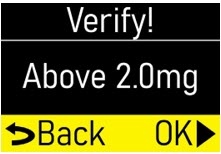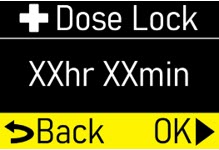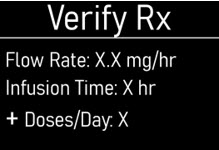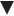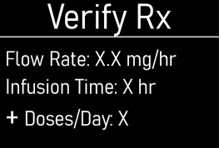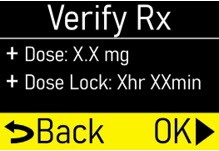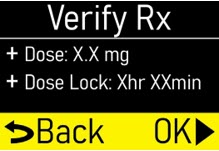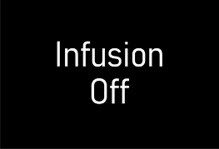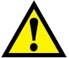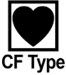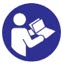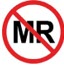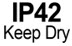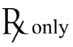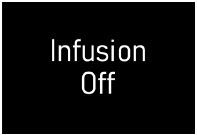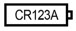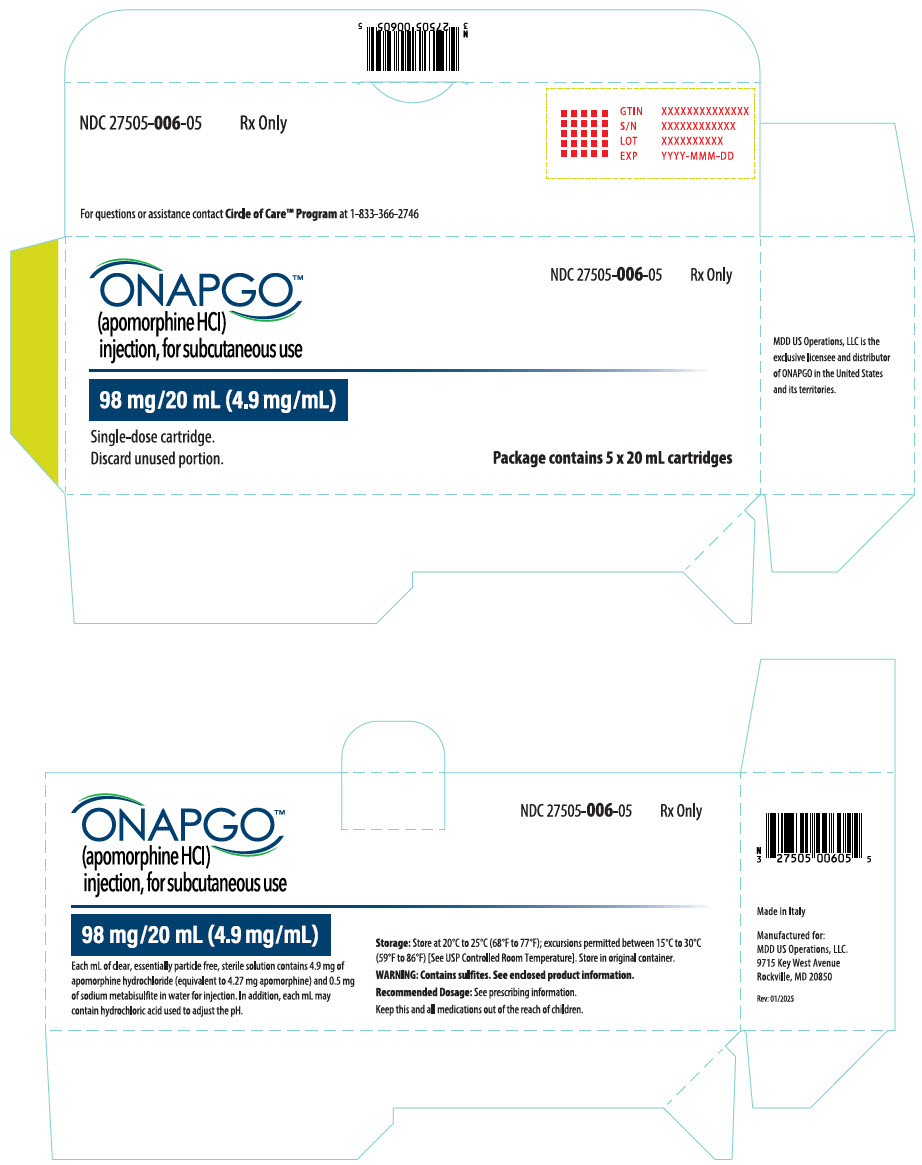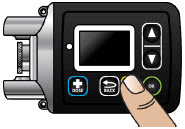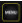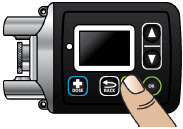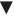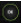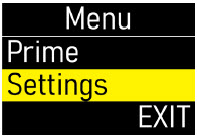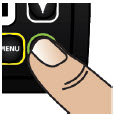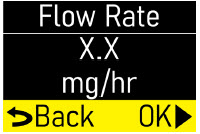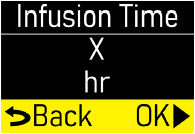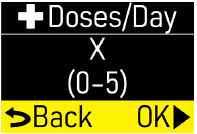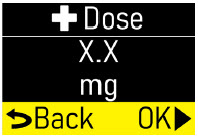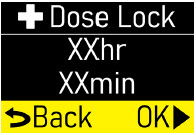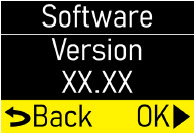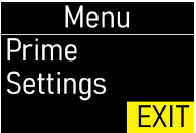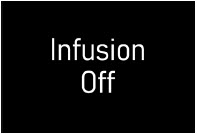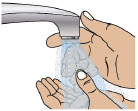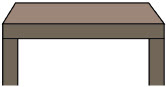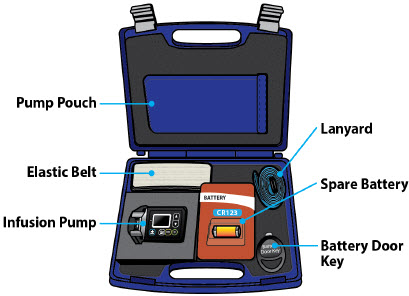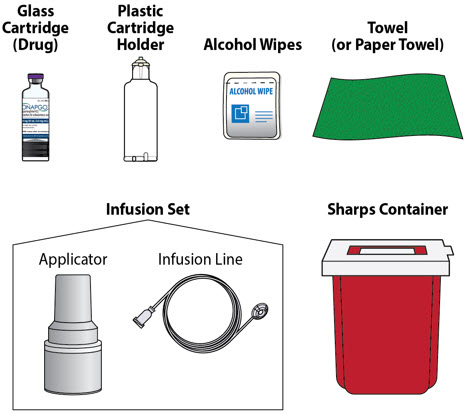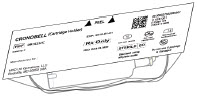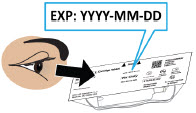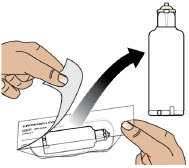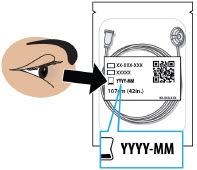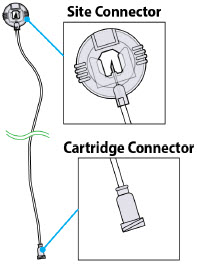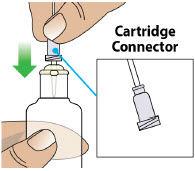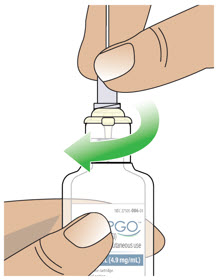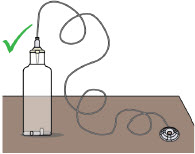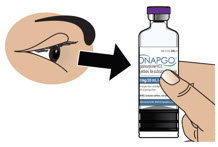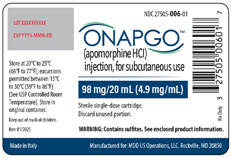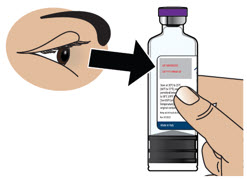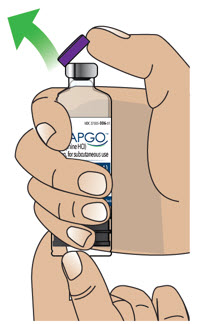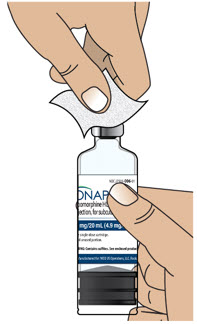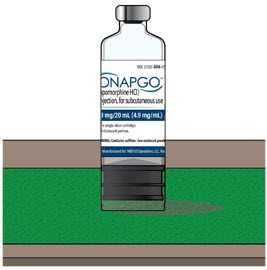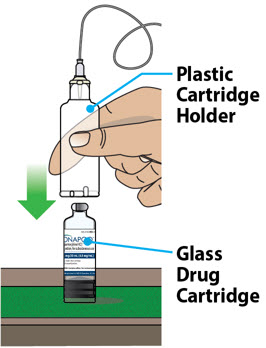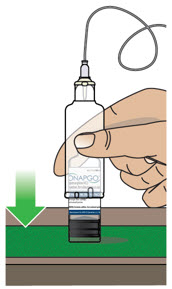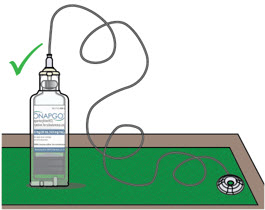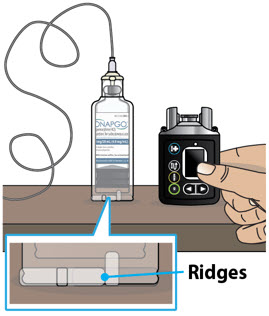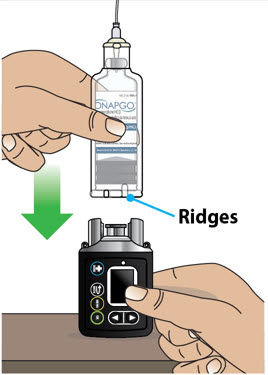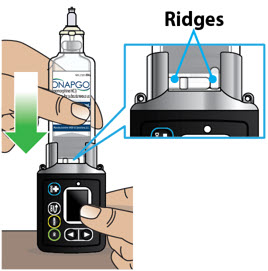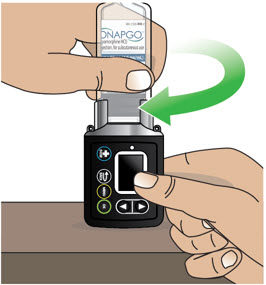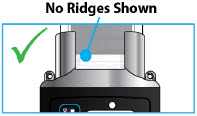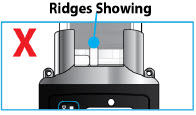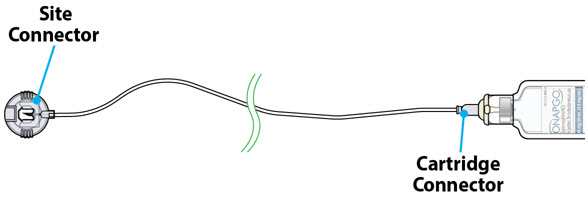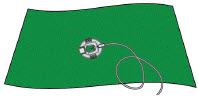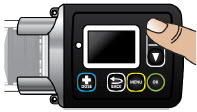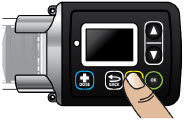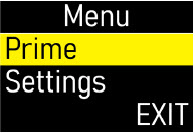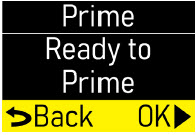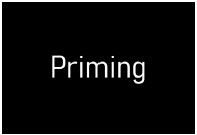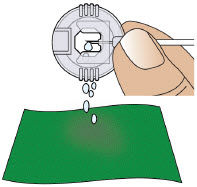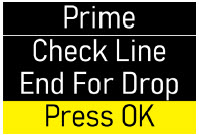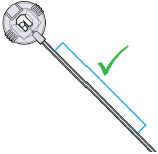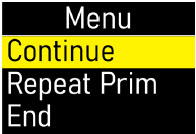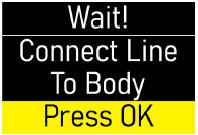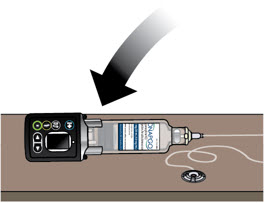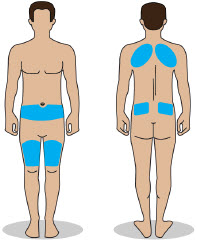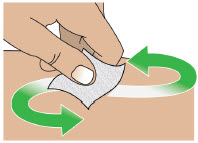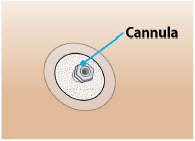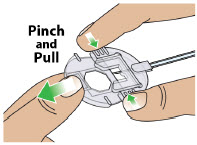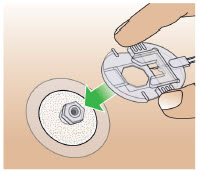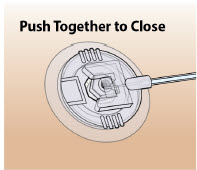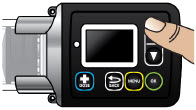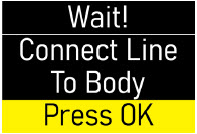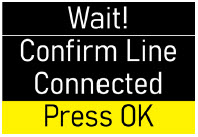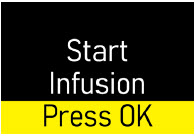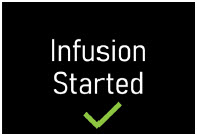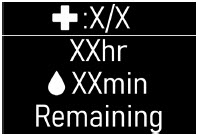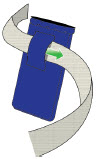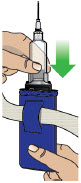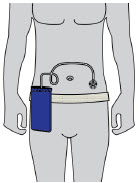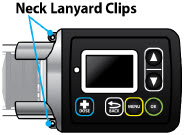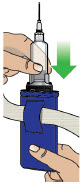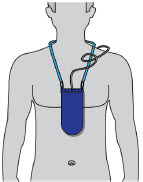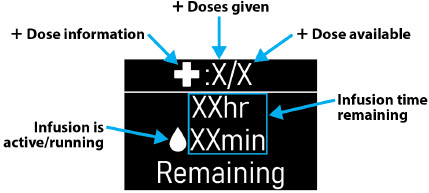 DRUG LABEL: ONAPGO
NDC: 27505-006 | Form: INJECTION, SOLUTION
Manufacturer: MDD US Operations, LLC, a subsidiary of Supernus Pharmaceuticals, Inc
Category: prescription | Type: HUMAN PRESCRIPTION DRUG LABEL
Date: 20260212

ACTIVE INGREDIENTS: APOMORPHINE HYDROCHLORIDE 4.9 mg/1 mL
INACTIVE INGREDIENTS: SODIUM METABISULFITE 0.5 mg/1 mL; HYDROCHLORIC ACID; WATER

HIGHLIGHTS OF PRESCRIBING INFORMATION

These highlights do not include all the information needed to use ONAPGO™ safely and effectively. See full prescribing information for ONAPGO™.
ONAPGO™ (apomorphine hydrochloride) injection, for subcutaneous use
Initial U.S. Approval: 2004

1 INDICATIONS AND USAGE

ONAPGO is a dopaminergic agonist indicated for the treatment of motor fluctuations in adults with advanced Parkinson's disease. (1)

2 DOSAGE AND ADMINISTRATION

- For subcutaneous use by infusion only. (2.1)
- Maximum recommended total daily dosage of ONAPGO, including the continuous dosage and any extra dose(s), is 98 mg generally administered over the waking day (e.g., 16 hours). (2.3)
- The recommended initial continuous dosage is 1 mg/hr with a maximum of 6 mg/hr for up to 16 hours per day. (2.3)
- The extra dose may be titrated in increments of 0.5 mg or 1 mg based on clinical response and tolerability. Subsequent extra doses are between 0.5 mg and 2 mg, with at least 3 hours between extra doses and a maximum of 3 extra doses per day. (2.3)
- Treatment with trimethobenzamide is recommended, starting 3 days prior to the first dose of ONAPGO, and should only be continued as long as necessary to control nausea and vomiting, and generally no longer than two months. (2.2, 5.2, 6.1, 17)
- ONAPGO is not substitutable for apomorphine products intended for intermittent use. (2.3)
- For patients with mild or moderate renal impairment, the recommended initial extra dose is 0.5 mg to 1 mg and should not exceed 1 mg. (2.5)

3 DOSAGE FORMS AND STRENGTHS

Injection: 98 mg/20 mL (4.9 mg/mL) of apomorphine hydrochloride in single-dose cartridges. (3)

4 CONTRAINDICATIONS

- Concomitant use of ONAPGO with 5HT3antagonists, including antiemetics (e.g., ondansetron, granisetron, dolasetron, palonosetron) and alosetron. (4, 7.1)
- Hypersensitivity to apomorphine or the excipients of ONAPGO, including sulfite (i.e., sodium metabisulfite). (4, 5.13)

5 WARNINGS AND PRECAUTIONS

- Subcutaneous use only; thrombus formation and pulmonary embolism have followed intravenous administration of ONAPGO. (5.1)
- May cause nausea and vomiting. (2.2, 5.2)
- Falling asleep during activities of daily living and daytime somnolence may occur. (5.3)
- May cause hypotension/orthostatic hypotension and syncope may occur. (5.4)
- May cause or increase the risk of falls. (5.5)
- May cause infusion site reactions and infections. Monitor and change infusion site every day. (2.4, 5.6)
- May cause hallucinations and psychotic-like behavior. (5.7)
- May cause dyskinesia or exacerbate pre-existing dyskinesia. (5.8)
- May cause hemolytic anemia. (5.9)
- May cause impulse control/ compulsive and impulsive behaviors. Consider dose reductions or stopping ONAPGO. (5.10)
- May cause cardiac events. (5.11)
- May prolong QTc and cause torsades de pointes or sudden death. (5.12)

6 ADVERSE REACTIONS

Most common adverse reactions (incidence ≥10% on ONAPGO and at least twice the rate of placebo) were infusion site nodule, nausea, somnolence, infusion site erythema, dyskinesia, headache, and insomnia. (6.1)

To report SUSPECTED ADVERSE REACTIONS, contact MDD US Operations, LLC, a subsidiary of Supernus Pharmaceuticals, Inc. at toll-free number 1-833-366-2746 or FDA at 1-800-FDA-1088 or www.fda.gov/medwatch.

7 DRUG INTERACTIONS

- Concomitant use of antihypertensive medications and vasodilators: increased risk for hypotension, falls, and injuries. (7.2)
- Dopamine antagonists such as neuroleptics or metoclopramide, may diminish the effectiveness of ONAPGO. (7.4)

8 USE IN SPECIFIC POPULATIONS

- Pregnancy: Based on animal data, may cause fetal harm. (8.1)

FULL PRESCRIBING INFORMATION

1 INDICATIONS AND USAGE

ONAPGO is indicated for the treatment of motor fluctuations in adults with advanced Parkinson's disease.

2 DOSAGE AND ADMINISTRATION

2.1 Important Information

- ONAPGO is indicated for subcutaneous use by infusion only [see Warnings & Precautions (5.1)] .
- Patients selected for treatment with ONAPGO should be capable of understanding and trained on using the delivery system, either themselves or with the assistance of a caregiver [see Healthcare Provider Instructions for Use and Patient Instructions for Use].
- ONAPGO initiation and dose titrations should be done under medical supervision.
- The prescribed dose of ONAPGO should be expressed in "mg/hr" for the continuous dosage and "mg" for an extra dose.

2.2 Premedication and Concomitant Medication

Because of the incidence of nausea and vomiting with ONAPGO, it is recommended that treatment with trimethobenzamide 300 mg three times a day start 3 days prior to the initial dose of ONAPGO [see Adverse Reactions (6.1)and Warnings and Precautions (5.2)] . Alternatively, consider starting ONAPGO therapy, without antiemetics, at 1 mg/hour and titrate based upon effectiveness and tolerance.

If trimethobenzamide is used, it should be continued only as long as necessary to control nausea and vomiting, and generally no longer than two months after initiation of treatment with ONAPGO, as trimethobenzamide increases the incidence of somnolence, dizziness, and falls in patients treated with ONAPGO [see Warnings and Precautions (5.2)] .

Based on reports of profound hypotension and loss of consciousness when apomorphine was administered with ondansetron, the concomitant use of apomorphine with drugs of the 5HT3antagonist class including antiemetics (e.g., ondansetron, granisetron, dolasetron, palonosetron) and alosetron are contraindicated [see Contraindications (4)] .

After starting ONAPGO, adjustment of concomitant anti-Parkinson's disease medications may be necessary.

2.3 Recommended Dosage

ONAPGO (apomorphine hydrochloride) is administered as a subcutaneous infusion with the ONAPGO pump [see Dosage and Administration (2.3), Healthcare Provider Instructions for Use, and Patient Instructions for Use].

The daily dosage is determined by individualized patient titration and is composed of a continuous dosage and as needed extra dose(s).

The maximum recommended total daily dosage of ONAPGO, including the continuous dosage and any extra dose(s), is 98 mg per day, generally administered over the waking day (e.g., 16 hours).

Continuous Dosage

The recommended initial continuous dosage (continuous infusion) of ONAPGO is 1 mg/hr. Titrate the continuous dosage, as needed, in 0.5 mg/hr to 1 mg/hr increments. Dose adjustments may be made daily, or at longer intervals, through the titration process. Patients in clinical studies used a mean of 4 mg/hr of ONAPGO. The maximum continuous dosage is 6 mg/hour administered over the waking day (e.g., 16 hours).

Extra Dose

Extra doses of ONAPGO may be used:

- upon starting in the morning; or
- when restarting the continuous dosage after a 1-hour or longer break in use (i.e., as a loading dose); or
- as a supplement to the continuous dosage to manage acute OFF symptoms that are not controlled

The extra dose may be titrated to clinical response and tolerability with adjustments in increments of 0.5 mg or 1 mg. Subsequent extra doses may be between 0.5 mg and 2 mg.

Administer no more than 3 extra doses per day over 16 hours with at least 3 hours between extra doses.

If 3 extra doses are routinely required during daily infusion, consider further adjustment of the continuous dosage.

The maximum recommended total daily dosage, including extra doses, is 98 mg during the waking day (e.g., 16 hours).

Other Apomorphine Medications

ONAPGO is not substitutable for apomorphine products intended for intermittent use. There is insufficient information about concomitant use of other apomorphine containing products with ONAPGO.

2.4 Preparation and Administration Instructions

Patients and caregivers should receive education and be trained on the proper use of ONAPGO and the device delivery system prior to first use [see Dosage and Administration (2.2)and Patient Instructions for Use].

- Visually inspect solution for particulate matter and discoloration prior to administration. Solution should be clear, almost colorless. Do not use if solution is discolored or contains particles.
- Keep the infusion site clean and use aseptic technique.
- Administer ONAPGO subcutaneously in one of the following areas:
  - Abdomen at least 2 inches away from the navel
  - Top of thigh
  - Lower back
  - Upper back, only when the infusion site is being prepared by a caregiver or healthcare provider
- Change the infusion site every day
- Do notselect an infusion site that is bruised, has bumps or nodules, or is irritated.
- A new single-dose cartridge and cartridge holder should be used each day. Discard unused portion.

2.5 Recommended Dosage in Patients with Renal Impairment

For patients with mild or moderate renal impairment, the recommended initial extra dose is 0.5 mg to 1 mg and should not exceed 1 mg [see Clinical Pharmacology (12.3)and Use in Specific Populations (8.6)]. No adjustment is needed for the continuous dose, maximum recommended daily dose, or subsequent extra doses after the initial extra dose [see Dosage and Administration (2.3)]. Patients with severe renal impairment have not been studied.

2.6 Discontinuation of ONAPGO

Sudden discontinuation or rapid dose reduction of ONAPGO could result in increased severity of Parkinson's disease motor symptoms. If possible, ONAPGO should be tapered before discontinuing.

3 DOSAGE FORMS AND STRENGTHS

Injection: 98 mg/20 mL (4.9 mg/mL) apomorphine hydrochloride is a clear, almost colorless solution available in a single-dose prefilled cartridge.

4 CONTRAINDICATIONS

ONAPGO is contraindicated in patients:

- Using concomitant 5HT3antagonists, including antiemetics (e.g., ondansetron, granisetron, dolasetron, palonosetron) and alosetron [see Drug Interactions (7.1)] . There have been reports of profound hypotension and loss of consciousness when apomorphine was administered with ondansetron.
- With hypersensitivity/allergic reaction to apomorphine or any of the excipients of ONAPGO, including sulfite (i.e., sodium metabisulfite). Angioedema or anaphylaxis may occur [see Warnings and Precautions (5.13)].

5 WARNINGS AND PRECAUTIONS

5.1 Serious Adverse Reactions After Intravenous Administration

Following intravenous administration of apomorphine, serious adverse reactions including thrombus formation and pulmonary embolism caused by intravenous crystallization of apomorphine have occurred. Do not administer ONAPGO intravenously.

5.2 Nausea and Vomiting

ONAPGO is known to cause nausea and vomiting, which may be severe. In Study 1 [see Clinical Studies (14)] 87% of patients were pretreated with an antiemetic. Twenty-two percent of patients treated with ONAPGO reported nausea and 7% reported vomiting, compared to 9% and 4%, respectively, of patients who received placebo. The ability of concomitantly administered antiemetic drugs (other than trimethobenzamide) to reduce apomorphine-associated nausea/vomiting has not been studied. Antiemetics with anti-dopaminergic actions (e.g., haloperidol, chlorpromazine, promethazine, prochlorperazine, metoclopramide) have the potential to worsen the symptoms in patients with PD and therefore the benefits and risks of treatment with these antiemetics should be carefully considered. The use of ONAPGO with 5HT3antiemetics is contraindicated.

5.3 Falling Asleep During Activities of Daily Living and Somnolence

Somnolence is commonly associated with ONAPGO .Patients treated with dopaminergic medications, including apomorphine, have also reported falling asleep while engaged in activities of daily living, including the operation of motor vehicles, which sometimes resulted in accidents. Patients may not perceive warning signs, such as excessive drowsiness, or they may report feeling alert immediately prior to the event. In the double-blind placebo-controlled trial (Study 1), somnolence was reported in 22% of patients treated with ONAPGO and 4% of patients in the placebo group.

Falling asleep while engaged in activities of daily living usually occurs in patients experiencing preexisting somnolence, although patients may not give such a history. Therefore, prescribers should reassess patients for drowsiness or sleepiness while using ONAPGO, especially because some of the events occur well after the start of treatment. Prescribers should also be aware that patients may not acknowledge drowsiness or sleepiness until directly questioned about drowsiness or sleepiness during specific activities.

Before initiating treatment with ONAPGO, advise patients of the risk of drowsiness and ask them about factors that could increase the risk with ONAPGO, such as concomitant sedating medications and the presence of sleep disorders. If a patient develops significant daytime sleepiness or falls asleep during activities that require active participation (e.g., conversations, eating, etc.), ONAPGO should ordinarily be discontinued. If a decision is made to continue ONAPGO, patients should be advised not to drive and to avoid other potentially dangerous activities. There is insufficient information to determine whether dose reduction will eliminate episodes of falling asleep while engaged in activities of daily living.

5.4 Syncope/Hypotension/Orthostatic Hypotension

Dopamine agonists, including ONAPGO, may cause orthostatic hypotension at any time, but especially during dose escalation. Patients with PD may also have an impaired capacity to respond to an orthostatic challenge. For these reasons, PD patients being treated with dopaminergic agonists should be monitored for signs and symptoms of orthostatic hypotension, especially during dose escalation, and should be informed of this risk.

When evaluated at various times after dosing in Study 1, patients undergoing titration of ONAPGO showed an increased incidence (from 4.5% pre-dose to 44.4% post-dose) of systolic orthostatic hypotension (≥ 20 mm Hg decrease upon standing) compared to placebo (7.1% pre-dose to 16.3% post-dose). Similarly, increased incidences of diastolic orthostatic hypotension (≥ 10 mm Hg decrease upon standing) were noted in patients titrated with ONAPGO (4.5% pre-dose to 44.4% post-dose) compared to placebo (11.9% pre-dose to 30.2% post-dose). Through the 12-week treatment period, these differences in incidence rates for systolic and diastolic orthostatic hypotension remained similar between ONAPGO and placebo patients. Patients in both ONAPGO and placebo groups developed severe systolic orthostatic hypotension (≥ 40 mm Hg decrease) and/or diastolic orthostatic hypotension (≥ 20 mm Hg decrease).

In Study 1, 13% of patients treated with ONAPGO reported hypotension or orthostatic hypotension compared to 2% of patients who received placebo [hypotension (7% vs 0%), orthostatic hypotension (4% vs 2%), and orthostatic intolerance (2% vs 0%)]. In the double-blind period of Study 1, one patient (2%) experienced a serious adverse event of hypotension and withdrew from the study compared to none in placebo.

Syncope has been reported in patients who have received subcutaneous apomorphine.

Patients with PD may also have an impaired capacity to respond to an orthostatic challenge. For these reasons, PD patients being treated with dopaminergic agonists ordinarily require careful monitoring for signs and symptoms of orthostatic hypotension, especially during dose escalation, and should be informed of this risk. Patients should avoid alcohol when using ONAPGO [see Drug Interactions (7.3)] . Patients taking ONAPGO should lie down before and after taking sublingual nitroglycerin. Other vasodilators and antihypertensives may also increase the hypotensive effects of ONAPGO. Monitor blood pressure for hypotension and orthostatic hypotension in patients taking ONAPGO with concomitant antihypertensive medications or vasodilators [see Drug Interactions (7.2)].

5.5 Falls

Patients with Parkinson's disease are at risk of falling due to underlying postural instability, possible autonomic instability, and syncope caused by the blood pressure lowering effects of the drugs used to treat Parkinson's disease. ONAPGO might increase the risk of falling by simultaneously lowering blood pressure and altering mobility [see Warnings and Precautions (5.4)and Clinical Pharmacology (12.2)]. Falls, including serious falls, have been reported in patients treated with apomorphine.

5.6 Infusion Site Reactions and Infections

ONAPGO can cause infusion site reactions and infections.

In Study 1, one or more infusion site reactions were reported in 63% of patients treated with ONAPGO and 15% in patients who received placebo. Various types of reactions at the infusion site have been reported including nodules, erythema, hematomas, inflammation, pruritus, swelling, discoloration, hemorrhage, hypersensitivity, induration, edema, pain, rash, or bruising [see Adverse Reactions (6.1)] . In Study 1, 2% of patients treated with ONAPGO and no patient who received placebo discontinued treatment because of an infusion site reaction.

Infusion site infections occurred in 4% of patients treated with ONAPGO compared to no patients who received placebo. The most frequent infusion site infection reported was cellulitis. If an infection is suspected at the infusion site, the cannula should be removed from the infusion site. If the cannula is removed for an infection, a new cannula should be placed at a new infusion site. In the event of a prolonged interruption of treatment with ONAPGO, the patient should be prescribed oral medications to treat their Parkinson's disease [see Dosage and Administration (2.4)].

5.7 Hallucinations/Psychotic-Like Behavior

In Study 1, 4% of patients treated with ONAPGO reported hallucinations compared to 4% of patients who received placebo. Psychotic disorder was reported in 2% of patients treated with ONAPGO compared to none who received placebo.

Postmarketing reports with intermittent subcutaneous apomorphine indicate that patients may experience new or worsening mental status and behavioral changes, which may be severe, including psychotic-like behavior after starting or increasing the dose of apomorphine. Other drugs prescribed to improve the symptoms of PD can have similar effects on thinking and behavior. This abnormal thinking and behavior can consist of one or more of a variety of manifestations, including paranoid ideation, delusions, hallucinations, confusion, disorientation, aggressive behavior, agitation, and delirium. Consider the risks and benefits prior to initiating treatment with ONAPGO in patients with a major psychotic disorder because of the risk of exacerbating psychosis. In addition, certain medications used to treat psychosis may exacerbate the symptoms of PD and may decrease the effectiveness of ONAPGO [see Drug Interactions (7.3)] .

5.8 Dyskinesia

ONAPGO may cause dyskinesia or exacerbate pre-existing dyskinesia. In Study 1, dyskinesia or worsening of dyskinesia was reported in approximately 15% of patients treated with ONAPGO compared to no patients who received placebo.

5.9 Hemolytic Anemia

Hemolytic anemia requiring hospitalization has been reported with apomorphine treatment in a postmarketing setting. Many of the reported cases included positive direct antiglobulin test (Coombs test), suggesting a potential immune-mediated hemolysis. Severe anemia, angina, and dyspnea have occurred with hemolytic anemia. Some patients were treated with high dose glucocorticoids or blood transfusions. Hemolytic anemia can occur at any time after apomorphine treatment. If a patient develops anemia while taking ONAPGO, consider a workup for hemolytic anemia. If hemolytic anemia occurs, consider discontinuing treatment with ONAPGO. In Study 1, hemolytic anemia was reported in 2% of patients treated with ONAPGO compared to no patient who received placebo.

5.10 Impulse Control/Compulsive Behaviors

Patients may experience intense urges to gamble, increased sexual urges, intense urges to spend money uncontrollably, and other intense urges and the inability to control these urges while taking one or more of the medications, including ONAPGO, that increase central dopaminergic tone and that are generally used for the treatment of PD. In some cases, although not all, these urges were reported to have stopped when the dose was reduced, or the medication was discontinued. Because patients may not recognize these behaviors as abnormal, it is important for prescribers to specifically ask patients or their caregivers about the development of new or increased gambling urges, sexual urges, uncontrolled spending, or other urges while being treated with ONAPGO. Physicians should consider dose reduction or stopping the medication if a patient develops such urges while taking ONAPGO

5.11 Cardiac Events

In Study 1, 4 patients treated with ONAPGO experienced cardiac disorders, including left bundle branch block (2%), myocardial infarction (2%), palpitations (2%), or tachycardia (2%), compared to no patients who received placebo. In patients treated with apomorphine subcutaneous injection, cardiac arrest and/or sudden death has occurred; some cases of angina and myocardial infarction occurred in close proximity to apomorphine dosing (within 2 hours), while other cases of cardiac arrest and sudden death were observed at times unrelated to dosing.

ONAPGO has been shown to reduce resting systolic and diastolic blood pressure and may have the potential to exacerbate cardiac (and cerebral) ischemia in patients with known cardiovascular and cerebrovascular disease. If patients develop signs and symptoms of cardiac or cerebral ischemia, prescribers should re-evaluate the continued use of ONAPGO.

5.12 QTc Prolongation and Potential for Proarrhythmic Effects

There is a dose-related prolongation of QTc interval after apomorphine exposure similar to that achieved with therapeutic doses of ONAPGO [see Clinical Pharmacology (12.2)] . In Study 1, 4% of patients treated with ONAPGO experienced prolonged QTc interval compared to none who received placebo.

Drugs that prolong the QTc interval have been associated with torsades de pointes and sudden death. The relationship of QTc prolongation to torsades de pointes is clearest for larger increases (20 msec and greater), but it is possible that smaller QTc prolongations may also increase risk, or increase it in susceptible individuals, such as those with hypokalemia, hypomagnesemia, bradycardia, concomitant use of other drugs that prolong the QTc interval, or genetic predisposition (e.g., congenital prolongation of the QT interval). Although torsades de pointes has not been observed in association with the use of ONAPGO at recommended doses in clinical studies, experience is too limited to rule out an increased risk. Palpitations and syncope may signal the occurrence of an episode of torsades de pointes.

The risks and benefits of ONAPGO treatment should be considered prior to initiating treatment with ONAPGO in patients with risk factors for prolonged QTc.

5.13 Hypersensitivity

In Study 1, 11% of patients treated with ONAPGO reported rash (4%), infusion site pruritus (4%), infusion site rash (2%), hypersensitivity (2%), or infusion site hypersensitivity (2%) compared to no patient who received placebo. Hypersensitivity/allergic reactions characterized by urticaria, rash, pruritus, and/or various manifestations of angioedema may occur because of ONAPGO or because of its sulfite excipient. ONAPGO contains sodium metabisulfite, a sulfite that may cause allergic-type reactions, including anaphylactic symptoms and life-threatening or less severe asthmatic episodes in certain susceptible people. The overall prevalence of sulfite sensitivity in the general population is unknown and probably low. Sulfite sensitivity is seen more frequently in asthmatic than in nonasthmatic people.

5.14 Fibrotic Complications

Cases of retroperitoneal fibrosis, pulmonary infiltrates, pleural effusion, pleural thickening, and cardiac valvulopathy have been reported in some patients treated with ergot-derived dopaminergic agents. While these complications may resolve when the drug is discontinued, complete resolution does not always occur. Although these adverse reactions are believed to be related to the ergoline structure of these dopamine agonists, whether other, non-ergot-derived dopamine agonists, such as ONAPGO, can cause these reactions is unknown.

5.15 Priapism

In clinical studies of intermittent apomorphine injection, painful erections were reported in 3 of 361 men treated with subcutaneous injection, and one patient withdrew from therapy because of priapism. Although no patients in the clinical studies required surgical intervention, severe priapism may require surgical intervention.

5.16 Retinal Pathology in Albino Rats

In a two-year carcinogenicity study of apomorphine in albino rat, retinal atrophy was detected at all subcutaneous doses tested (up to 0.8 mg/kg/day or 2 mg/kg/day in males or females, respectively; less than the maximum recommended human dose (MRHD) of 98 mg/day on a body surface area [mg/m^2] basis). Retinal atrophy/degeneration has been observed in albino rats treated with other dopamine agonists for prolonged periods (generally during two-year carcinogenicity studies). Retinal findings were not observed in a 39-week subcutaneous toxicity study of apomorphine in monkey at doses up to 1.5 mg/kg/day, a dose similar to the MRHD on a mg/m^2basis. The clinical significance of the finding in rat has not been established but cannot be disregarded because disruption of a mechanism that is universally present in vertebrates (e.g., disk shedding) may be involved.

6 ADVERSE REACTIONS

The following clinically significant adverse reactions are described elsewhere in the labeling:

- Serious Adverse Reactions After Intravenous Administration [see Warnings and Precautions (5.1)]
- Nausea and Vomiting [see Warnings and Precautions (5.2)]
- Falling Asleep During Activities of Daily Living and Somnolence [see Warnings and Precautions (5.3)]
- Syncope/Hypotension/Orthostatic Hypotension [see Warnings and Precautions (5.4)]
- Falls [see Warnings and Precautions (5.5)]
- Infusion Site Reactions and Infections [see Warnings and Precautions (5.6)]
- Hallucinations/Psychotic-Like Behavior [see Warnings and Precautions (5.7)]
- Dyskinesia [see Warnings and Precautions (5.8)]
- Hemolytic Anemia [see Warnings and Precautions (5.9)]
- Impulse Control/Compulsive Behaviors [see Warnings and Precautions (5.10)]
- Cardiac Events [see Warnings and Precautions (5.11)]
- QTc Prolongation and Potential for Proarrhythmic Effects [see Warnings and Precautions (5.12)]
- Hypersensitivity [see Warnings and Precautions (5.13)]
- Fibrotic Complications [see Warnings and Precautions (5.14)]
- Priapism [see Warnings and Precautions (5.15)]

6.1 Clinical Trials Experience

Because clinical trials are conducted under widely varying conditions, adverse reaction rates observed in the clinical trials of a drug cannot be directly compared to rates in the clinical trials of another drug and may not reflect the rates observed in clinical practice. A total of 197 Parkinson's disease patients were exposed to ONAPGO in Study 1 and subsequent open-label studies.

In Study 1 [see Clinical Studies (14)], the most common adverse reactions (incidence 10% or greater in patients treated with ONAPGO and at a rate at least twice the placebo rate) were infusion site nodule, nausea, somnolence, infusion site erythema, dyskinesia, headache, and insomnia.

Table 1 presents adverse reactions that occurred in ≥5% of patients treated with ONAPGO and that occurred more frequently than placebo in patients who were enrolled in Study 1.

Table 1: Adverse Reactions Reported by ≥5% of Patients Treated with ONAPGO and More Frequently than Placebo in Study 1
 | ONAPGO [Variable doses [see Dosage and Administration (2.3)]] N=54 % | Placebo N=53 %
Infusion site nodule | 44 | 0
Nausea | 22 | 9
Somnolence | 22 | 4
Infusion site erythema | 17 | 4
Dyskinesia | 15 | 0
Headache | 13 | 4
Insomnia | 11 | 2
Dizziness | 9 | 4
Hypotension | 7 | 0
Asthenia | 7 | 0
Fatigue | 7 | 2
Constipation | 7 | 6
Vomiting | 7 | 4

Infusion Site Reactions

In Study 1, infusion site reactions were most commonly reported as nodule formation (44% of patients treated with ONAPGO compared to no patients who received placebo) or erythema (17% of patients treated with ONAPGO compared to 4% of patients who received placebo).

Less Common Adverse Reactions

Other adverse reactions, including hallucinations, psychotic disorder, impulse control disorder, prolonged QT interval, and infusion site infections [see Warnings and Precautions (5.6)] , have been reported in patients treated with ONAPGO [see Warnings and Precautions (5.7, 5.10. 5.12)].

Adverse Reactions Leading to Discontinuation of ONAPGO Treatment

Six (11%) of patients treated with ONAPGO reported one of the following adverse reactions as the reason for discontinuing from Study 1: nausea, orthostatic intolerance, visual hallucination, gait disturbance, infusion site nodule, and hypotension. None of the patients who received placebo discontinued from Study 1 because of an adverse reaction.

6.2 Postmarketing Experience

The following adverse reactions have been identified during post-approval use of apomorphine. Because these reactions are reported voluntarily from a population of uncertain size, it is not always possible to reliably estimate their frequency or establish a causal relationship to drug exposure.

Hematologic and Lymphatic Systems: hemolytic anemia [see Warnings and Precautions (5.9)]

7 DRUG INTERACTIONS

7.1 5HT3Antagonists

Based on reports of profound hypotension and loss of consciousness when apomorphine was administered with ondansetron, the concomitant use of ONAPGO with 5HT3antagonists, including antiemetics (e.g., ondansetron, granisetron, palonosetron) and alosetron, is contraindicated [see Warnings and Precautions (5.4)].

7.2 Antihypertensive Medications and Vasodilators

In clinical studies with intermittent subcutaneous administration of apomorphine, the following adverse reactions were experienced more commonly in patients receiving concomitant antihypertensive medications or vasodilators (n=94) than in patients not receiving these medications (n=456): hypotension (10% vs 4%) myocardial infarction (3% vs 1%), [see Warnings and Precautions (5.4, 5.11)].

In a study of healthy subjects, concomitant administration of 0.4 mg sublingual nitroglycerin with subcutaneous apomorphine caused greater decreases in blood pressure than with subcutaneous apomorphine alone [see Clinical Pharmacology (12.3)]. Patients treated with ONAPGO should lie down before and after taking sublingual nitroglycerin to decrease the potential risks associated with hypotension .

7.3 Alcohol

In a study of healthy subjects, concomitant administration of high dose (0.6 g/kg) or low dose (0.3 g/kg) ethanol with apomorphine caused greater decreases in blood pressure than with apomorphine alone [see Clinical Pharmacology (12.3)] . Patients should be advised not to consume alcohol while treated with ONAPGO because it may cause greater decreases in blood pressure [see Warnings and Precautions (5.4)] .

7.4 Dopamine Antagonists

Because ONAPGO is a dopamine agonist, it is possible that concomitant use of dopamine antagonists, such as the neuroleptics (phenothiazines, butyrophenones, thioxanthenes) or metoclopramide, may diminish the effectiveness of ONAPGO. Antiemetics with anti-dopaminergic actions should be avoided [see Warnings and Precautions (5.2)]. Patients with major psychotic disorders, treated with neuroleptics, should be treated with dopamine agonists only if the potential benefits outweigh the risks [see Warnings and Precautions (5.7)].

7.5 Drugs Prolonging the QT/QTc Interval

Caution should be exercised when prescribing ONAPGO concomitantly with drugs that prolong the QT/QTc interval [see Warnings and Precautions (5.12)and Clinical Pharmacology (12.2)] .

8 USE IN SPECIFIC POPULATIONS

8.1 Pregnancy

Risk Summary

There are no adequate data on the developmental risk associated with use of ONAPGO in pregnant women. In animal reproduction studies, apomorphine had adverse developmental effects in rats (increased neonatal deaths) and rabbits (increased incidence of malformation) when administered during pregnancy at clinically relevant doses. These doses were also associated with maternal toxicity. In the U.S. general population, the estimated background risk of major birth defects and miscarriage in clinically recognized pregnancies is 2% to 4% and 15% to 20%, respectively. The background risk of major birth defects and miscarriage for the indicated population is unknown.

Data

Animal Data

No adverse developmental effects were observed when apomorphine (0.3, 1, or 3 mg/kg/day) was administered by subcutaneous injection to pregnant rats throughout organogenesis; the highest dose tested is less than the maximum recommended human dose (MRRD) of 98 mg on a mg/m^2basis. Administration of apomorphine (0.3, 1, or 3 mg/kg/day) by subcutaneous injection to pregnant rabbits throughout organogenesis resulted in an increased incidence of malformations of the heart and/or great vessels at the mid and high doses; maternal toxicity was observed at the highest dose tested. The no-effect dose (0.3mg/kg/day) for adverse effects is less than the MRHD on a mg/m^2basis.

Apomorphine (0.3, 1, or 3 mg/kg/day), administered by subcutaneous injection to female rats throughout gestation and lactation, resulted in increased offspring mortality at the highest dose tested, which was associated with maternal toxicity. There were no effects on developmental parameters or reproductive performance in surviving offspring. The no-effect dose (1 mg/kg/day) for developmental toxicity is less than the MRHD on a mg/m^2basis.

8.2 Lactation

Risk Summary

There are no data on the presence of apomorphine in human milk, the effects on the breastfed infant, or the effects on milk production. The developmental and health benefits of breastfeeding should be considered along with the mother's clinical need for ONAPGO and any potential adverse effects on the breastfed infant from ONAPGO or from the underlying maternal condition.

8.4 Pediatric Use

Safety and effectiveness in pediatric patients have not been established.

8.5 Geriatric Use

In general, dose selection for an elderly patient should be cautious, usually starting at the low end of the dosing range, reflecting the greater frequency of decreased hepatic, renal, or cardiac function, and of comorbid disease or other drug therapy.

Clinical studies of ONAPGO did not include sufficient numbers of patients aged 65 and over to determine whether they respond differently from younger subjects. Clinical experience with intermittent subcutaneous use of apomorphine has shown that the following adverse reactions were reported more frequently in patients 65 years of age or older (n=311) compared to patients less than 65 years of age (n=239): confusion; hallucinations; serious adverse reactions (life-threatening events or events resulting in hospitalization and/or increased disability); falls (experiencing bone and joint injuries); cardiovascular events; respiratory disorders; gastrointestinal events; and discontinuation of treatment as a result of one or more adverse reactions.

8.6 Renal Impairment

The initial extra dose of ONAPGO should not exceed 1 mg in patients with mild or moderate renal impairment because of increased apomorphine concentration and exposure (Cmaxand AUC) in these patients. Studies in patients with severe renal impairment have not been conducted [see Dosage and Administration (2.5)and Clinical Pharmacology (12.3)].

8.7 Hepatic Impairment

Exercise caution and closely monitor if ONAPGO is administered to patients with mild or moderate hepatic impairment because of increased apomorphine concentration and exposure (Cmaxand AUC) in these patients. Studies in patients with severe hepatic impairment have not been conducted [see Clinical Pharmacology (12.3)] .

9 DRUG ABUSE AND DEPENDENCE

9.1 Controlled Substance

ONAPGO contains apomorphine, which is not a controlled substance.

9.2 Abuse

In premarketing clinical experience, apomorphine did not reveal any tendency for a withdrawal syndrome or any drug-seeking behavior. However, there are rare postmarketing reports of abuse of medications containing apomorphine. In general, these reports consist of patients taking increasing doses of medication in order to achieve a euphoric state. Abuse is the intentional, non-therapeutic use of a drug, even once, for its desirable psychological or physiological effects.

11 DESCRIPTION

ONAPGO (apomorphine hydrochloride) contains apomorphine hydrochloride hemihydrate, a non-ergoline dopamine agonist. It is chemically designated as 6aβ-aporphine-10,11-diol hydrochloride hemihydrate with a molecular formula of C17H17NO2∙HCl∙½H2O. Its structural formula and molecular weight are:

Apomorphine hydrochloride hemihydrate appears as minute, white or grayish-white glistening crystals or as white powder that is soluble in water at 80°C. ONAPGO injection is a clear, almost colorless, sterile solution for subcutaneous infusion and is available in 98 mg/20 mL (4.9 mg/mL) single-dose prefilled cartridges. The solution has a pH of 3.0 -4.0. Each mL contains 4.9 mg of apomorphine hydrochloride (equivalent to 4.27 mg apomorphine) and 0.5 mg of sodium metabisulfite in water for injection. In addition, each mL may contain hydrochloric acid used to adjust the pH.

12 CLINICAL PHARMACOLOGY

12.1 Mechanism of Action

ONAPGO is a non-ergoline dopamine agonist with high in vitro binding affinity for the dopamine D4 receptor, and moderate affinity for the dopamine D2, D3, and D5, and adrenergic α1D, α2B, α2C receptors. The precise mechanism of action of ONAPGO as a treatment for Parkinson's disease is unknown, although it is believed to be due to stimulation of post-synaptic dopamine D2-type receptors within the caudate-putamen in the brain.

12.2 Pharmacodynamics

Prolongation of the QTc Interval and Cardiac Electrophysiology

In a thorough QT study, the mean increase in QTcF was 12.5 ms (90% two-sided upper confidence interval = 18.0 ms) after administration of a continuous dose of ONAPGO 6 mg/hr (maximum recommended infusion rate) in healthy subjects. A mean increase in QTcF of 14.6 ms (90% two-sided confidence interval = 20.1 ms) was observed at a dose and exposure similar to that expected with the maximum recommended total daily dosage of 98 mg. The maximum placebo-corrected increase in heart rate was 14.1 bpm (90% two-sided upper confidence interval = 17.4 bpm) at the dose and exposure similar to that expected with the maximum recommended total daily dose of 98 mg.

12.3 Pharmacokinetics

Absorption

After subcutaneous administration, apomorphine appears to have bioavailability equal to that of intravenous administration. Steady-state concentrations are reached in approximately two hours after initiation of a continuous dose. If an extra dose is administered at the initiation of the continuous dose [see Dosage and Administration (2.3)] , time to reach half (50%) of infusion steady-state concentrations can be shortened by 50-75%. If an extra dose is administered two hours or later following initiation of a continuous dose, the supplemental exposure from the extra dose reaches peak concentration in 20-40 minutes.

Distribution and Binding

The plasma-to-whole blood apomorphine concentration ratio is equal to one. Mean (range) apparent volume of distribution was 218 L (123 to 404 L). Protein binding in humans is 89% and concentration independent.

Elimination

The mean apparent clearance of apomorphine from plasma is 261 to 280 L/hr for ONAPGO with infusion rates ranging from 2 to 6 mg/hr. After administration of an extra dose, the mean elimination half-life is approximately 40 minutes.

Metabolism

Apomorphine metabolism is primarily via conjugation. Within 0.5 hours of administering a subcutaneous dose of^14C-apomorphine, only 8.3% of plasma radioactivity was apomorphine, while 83% was associated with the apomorphine sulfate, 3.5% with apomorphine glucuronide, and 1% with nor-apomorphine glucuronide.

Excretion

Eighty-six percent of the subcutaneously administered dose of^14C-apomorphine was recovered in the urine within 48 hours as apomorphine sulfate, apomorphine glucuronide and nor-apomorphine glucuronide. Another 4.6% of the administered dose was recovered in the feces over 144 hours as apomorphine sulfate, apomorphine glucuronide, and apomorphine.

Specific Populations

No clinically significant differences in the pharmacokinetics of apomorphine were observed based on age, gender, weight, duration of Parkinson's disease, levodopa dose, or duration of therapy.

Renal Impairment

In a study comparing patients with renal impairment (moderately impaired as determined by estimated creatinine clearance) to healthy matched volunteers, the AUC0-infand Cmaxwere increased by approximately 16% and 50%, respectively, following a single subcutaneous administration of apomorphine into the abdominal wall. The mean time to peak concentrations and the mean terminal half-life of apomorphine were unaffected by the renal status of the individual. Studies in patients with severe renal impairment have not been conducted [see Dosage and Administration (2.5)and Use in Specific Populations (8.6)] .

Hepatic Impairment

In a study comparing patients with hepatic impairment (moderately impaired as determined by the Child-Pugh classification method) to healthy matched volunteers, the AUC0-infand Cmaxvalues were increased by approximately 10% and 25%, respectively, following a single subcutaneous administration of apomorphine into the abdominal wall. Studies in patients with severe hepatic impairment have not been conducted [see Use in Specific Populations (8.7)] .

Drug Interaction Studies

Carbidopa/levodopa

Pharmacokinetics of levodopa were unchanged when subcutaneous apomorphine and levodopa were co-administered in patients. However, motor response differences were significant.

Ethanol and Nitroglycerin

Co-administration of low dose ethanol (0.3 g/kg), or nitroglycerin (0.4 mg) with an apomorphine injection dose of 6 mg in healthy individuals did not have a significant impact on the pharmacokinetics of apomorphine, but high dose ethanol (0.6 g/kg), equivalent to approximately 3 standardized alcohol-containing beverages, increased the Cmaxof apomorphine by about 63%. The hypotensive effect of apomorphine was increased by the concomitant use of alcohol or of sublingual nitroglycerin. When high-dose ethanol (0.6 g/kg) and subcutaneous apomorphine were concomitantly administered to healthy subjects, the mean largest decrease (the mean of each subject's largest drop in blood pressure measured within the 6-hour period following administration of subcutaneous apomorphine) for supine systolic and diastolic blood pressure was 9.1 mm Hg and 10.5 mm Hg, respectively. The mean largest standing systolic and diastolic blood pressure decrease was 11.3 mm Hg and 12.6 mm Hg, respectively. In some individuals, the decrease was as high as 61 mm Hg and 51 mm Hg, respectively, for standing systolic and diastolic blood pressure [see Warnings and Precautions (5.4), Drug Interactions (7.2, 7.3)].

Other Drugs Eliminated Via Hepatic Metabolism

Based upon an in vitrostudy, cytochrome P450 enzymes play a minor role in the metabolism of apomorphine. In vitrostudies have also demonstrated that drug interactions are unlikely due to apomorphine acting as a substrate, an inhibitor, or an inducer of cytochrome P450 enzymes.

COMT Interactions

A pharmacokinetic interaction of ONAPGO with catechol-O-methyl transferase (COMT) inhibitors or drugs metabolized by this route is unlikely because apomorphine appears not to be metabolized by COMT.

13 NONCLINICAL TOXICOLOGY

13.1 Carcinogenesis, Mutagenesis, Impairment of Fertility

Carcinogenesis

Lifetime carcinogenicity studies of apomorphine were conducted in male (0.1, 0.3, or 0.8 mg/kg/day) and female (0.3, 0.8, or 2 mg/kg/day) rats. Apomorphine was administered by subcutaneous injection for 22 months or 23 months, respectively. In males, there was an increase in Leydig cell tumors at the highest dose tested. This finding is of questionable significance because the endocrine mechanisms believed to be involved in the production of Leydig cell tumors in rats are not relevant to humans. No drug-related tumors were observed in females. The highest doses tested in males and females are less than the maximum recommended human dose (MRHD) on a mg/m^2basis.

In a 26-week carcinogenicity study in p53-knockout transgenic mice, there was no evidence of carcinogenic potential when apomorphine was administered by subcutaneous injection at doses up to 20 mg/kg/day in males or 40 mg/kg/day in females.

Mutagenesis

Apomorphine was mutagenic in the in vitrobacterial reverse mutation (Ames) and the in vitromouse lymphoma tkassays. Apomorphine was clastogenic in the in vitrochromosomal aberration assay in human lymphocytes and in the in vitromouse lymphoma tkassay. Apomorphine was negative in the in vivomicronucleus assay in mice.

Impairment of Fertility

Apomorphine was administered subcutaneously at doses up to 3 mg/kg/day to male and female rats prior to and throughout the mating period and continuing in females through gestation day 6. There was no evidence of adverse effects on fertility or on early fetal viability. The highest dose tested is less than the MRHD on a mg/m^2basis. A significant decrease in testis weight was observed in a 39-week study in cynomolgus monkey at all subcutaneous doses tested (0.3, 1, or 1.5 mg/kg/day); the lowest dose tested is less than the MRHD on a mg/m^2basis.

In a published fertility study, apomorphine was administered to male rats at subcutaneous doses of 0.2, 0.8, or 2 mg/kg prior to and throughout the mating period. Fertility was reduced at the highest dose tested.

14 CLINICAL STUDIES

Study 1 (NCT02006121) was a multicenter, parallel-group, double-blind, randomized, placebo-controlled trial to evaluate the efficacy and safety of ONAPGO subcutaneous infusion in patients with Parkinson's disease who had motor fluctuations while receiving carbidopa/levodopa and other concomitant medications to treat PD. The study design included a double-blind, 12-week treatment period, inclusive of 1-4 weeks of dose titration and then continued treatment with study medication at an individualized, stable dosage. Patients then had the option to receive ONAPGO in a 52-week, open-label treatment period.

The modified intent-to-treat (mITT) population included 53 patients treated with ONAPGO and 51 patients who received placebo. At baseline, patients experienced OFF episodes averaging ≥3 hours per day. In the mITT population, the mean age was 63.4 years, 62% were male, and 100% were White. At baseline, all patients were taking at least one concomitant medication to treat PD (e.g., dopamine agonist 87%, COMT-inhibitor 58%, MAO-B inhibitor 40%, amantadine 27%) in addition to oral immediate or extended-release levodopa plus a dopa decarboxylase inhibitor. The mean duration of PD was 11.9 years in the ONAPGO-treated group and 10.8 years in the placebo-treated group.

During titration, adjustments in concomitant medications to treat PD were made when clinically indicated. All patients treated with ONAPGO in the double-blind study were maintained on levodopa.

The primary efficacy endpoint for Study 1 was the change in total daily OFF time assessed from baseline to the end of the 12-week treatment period based on patient diaries. A key secondary endpoint was the change in daily ON time without troublesome dyskinesia from baseline to the end of the 12-week treatment period. There was a statistically significant reduction in the amount of daily OFF time in patients treated with ONAPGO compared to placebo (p=0.0114; see Table 2). There was also a statistically significant increase in daily ON time without troublesome dyskinesia in patients treated with ONAPGO compared to placebo (p=0.0188; see Table 3).

Table 2: Change From Baseline to Week 12 in Mean Total Daily OFF Time in Study 1 (mITT population)
 | N | Baseline (hours) (mean ± SD) | LS Mean Change from Baseline at Week 12 (hours) (mean ± SE) | LSD [Least squares difference from placebo; a negative value indicates improvement (reduction in OFF time)] vs Placebo (95% CI) [95% CI: 95% Confidence Interval] p-value
Placebo | 51 | 6.72 ± 2.547 | -0.90 ± 0.416 | --
ONAPGO | 53 | 6.69 ± 2.224 | -2.55 ± 0.487 | -1.65 (-2.91, -0.38) p=0.0114

Table 3: Change From Baseline to Week 12 in Mean Daily ON Time Without Troublesome Dyskinesia in Study 1 (mITT population)
 | N | Baseline (hours) (mean ± SD) | LS Mean Change from Baseline at Week 12 (hours) (mean ± SE) | LSD [Least squares difference from placebo; a positive value indicates improvement (increase in ON time without troublesome dyskinesia)] vs Placebo (95% CI) [95% CI: 95% Confidence Interval] p-value
Placebo | 51 | 8.64 ± 2.496 | 1.12 ± 0.500 | --
ONAPGO | 53 | 8.56 ± 2.329 | 2.76 ± 0.471 | 1.64 (0.28, 3.00) p=0.0188

In addition, the time course showed numerically greater improvement in daily OFF time and daily ON time without troublesome dyskinesia in patients treated with ONAPGO compared to placebo, at all post-baseline timepoints (Figure 2).

Figure 2: Mean Change from Baseline in Daily OFF Time and ON Time Without Troublesome Dyskinesia

A patient reported outcome, the Patient Global Impression of Change (PGIC) was also assessed. The PGIC evaluates the change in Parkinson's disease symptoms as perceived by the patient in a seven-point single-item scale ranging from 'very much worse' to 'very much improved' (Figure 3).

Figure 3: Week 12 Patient Global Impression of Change

16 HOW SUPPLIED/STORAGE AND HANDLING

16.1 How Supplied

ONAPGO injection is supplied as one carton (NDC 27505-006-05) that contains five single-dose prefilled glass cartridges, each containing 98 mg/20 mL (4.9 mg/mL) apomorphine hydrochloride as a clear, almost colorless solution.

The ONAPGO Pump Kit, ONAPGO Cartridge Holders, and appropriate infusion sets are supplied separately.

16.2 Storage and Handling

Store at 20°C to 25°C (68°F to 77°F); excursions permitted between 15°C to 30°C (59°F to 86°F) [see USP Controlled Room Temperature].

17 PATIENT COUNSELING INFORMATION

Advise the patient to read the FDA-approved patient labeling (Patient Information and Instructions for Use).

Administration Information

Refer patients to the Instructions for Use for complete administration instructions. Inform patients of aseptic technique and of subcutaneous administration site selection and rotation [see Dosage and Administration (2.4)].

Advise patients that a new single-dose cartridge and cartridge holder and a new infusion line should be used each day.

Advise patients that ONAPGO is intended only for subcutaneous use and must not be given intravenously because of the risk of serious complications, such as thrombus formation and pulmonary embolism due to crystallization [see Warnings and Precautions (5.1)] .

Hypersensitivity/Allergic Reactions

Advise patients that hypersensitivity/allergic reactions characterized by urticaria, rash, pruritus, and/or various manifestations of angioedema may occur because of ONAPGO or any of its excipients, including a sulfite (i.e., sodium metabisulfite). Inform patients with a sulfite sensitivity that they may experience various allergic-type reactions, including anaphylactic symptoms and life-threatening asthmatic attacks [see Warnings and Precautions (5.13)] . Advise patients who experience any hypersensitivity/allergic reaction to ONAPGO that they should not take ONAPGO again [see Contraindications (4)].

Nausea and Vomiting

Advise patients that they may experience nausea and vomiting, which may be severe. Advise patients that their ONAPGO dosage may be adjusted to start at 1mg/hr, and titration can be based upon effectiveness and tolerability. Treatment with an antiemetic that is a non-5HT3 antagonist may be used if needed. Oral trimethobenzamide 300 mg 3 times per day for 3 days prior to starting ONAPGO infusion has been used in clinical studies to help lessen these symptoms. Advise patients that ONAPGO taken with trimethobenzamide may increase the risk for somnolence, dizziness, and falls, and to consult their healthcare provider before discontinuing trimethobenzamide [see Warnings and Precautions (5.2)].

Falling Asleep Suddenly and Sedation/Sleepiness

Alert patients to the potential sedating effects of ONAPGO, including somnolence and falling asleep while engaged in activities of daily living. Instruct patients not to drive a car or engage in other potentially dangerous activities until they have gained sufficient experience with ONAPGO to gauge whether or not it affects their mental and/or motor performance adversely. Advise patients that if increased somnolence or episodes of falling asleep during activities of daily living (e.g., watching television, passenger in a car, etc.) occur, they should not drive or participate in potentially dangerous activities until they have contacted their physician [see Warnings and Precautions (5.3)].

Hypotension/Orthostatic Hypotension

Advise patients that they may develop postural (orthostatic) hypotension with or without symptoms such as dizziness, nausea, syncope, and sometimes sweating. Hypotension and/or orthostatic symptoms may occur more frequently during initial therapy or with an increase in dose at any time (cases have been seen after months of treatment). Instruct patients to rise slowly after sitting or lying down while using ONAPGO. Inform patients that alcohol and nitroglycerin (and possibly other vasodilators and antihypertensive medications) may worsen the potential effects of hypotension caused by ONAPGO [see Warnings and Precautions (5.4)]. Instruct patients ideally to lie down before taking sublingual nitroglycerin and to remain supine and avoid standing for at least 45 minutes after nitroglycerin. Instruct patients to avoid alcohol while using ONAPGO.

Falls

Alert patients that they may have increased risk for falling when using ONAPGO [see Warnings and Precautions (5.5)].

Infusion Site Reactions and Infections

Inform patients that infusion of ONAPGO may result in infusion site reactions, including, but not limited to nodules, erythema, bruising, and infection. Infusion site infections were reported in <5% of patients on ONAPGO in clinical trials [see Warnings and Precautions (5.6)and Adverse Reactions (6.1)] . Instruct patients to change the infusion site every day and to observe proper aseptic technique [see Dosage and Administration (2.4)and Instructions for Use] .

Hallucinations and/or Psychotic-Like Behavior

Inform patients that ONAPGO may cause hallucinations or other manifestations of psychotic-like behavior. Advise patients to inform their healthcare provider if they have a major psychotic disorder or are taking any treatments for psychosis. Patients with a major psychotic disorder should also be aware that many treatments for psychosis may decrease the effectiveness of ONAPGO [see Warnings and Precautions (5.7)] .

Dyskinesia

Inform patients that ONAPGO may cause and/or exacerbate pre-existing dyskinesia [see Warnings and Precautions (5.8)].

Hemolytic Anemia

Inform patients and caregivers that hemolytic anemia may occur and to contact their healthcare provider if they develop any signs or symptoms [see Warnings and Precautions (5.9)] .

Impulse Control / Compulsive Behaviors

Patients and their caregivers should be alerted to the possibility that they may experience intense urges to spend money uncontrollably, intense urges to gamble, increased sexual urges, binge eating and/or other intense urges and the inability to control these urges while using ONAPGO [see Warnings and Precautions (5.10)].

Cardiac Events

Inform patients that ONAPGO may cause cardiac (and cerebral) ischemia, and these outcomes could possibly be related to significant hypotension/orthostatic hypotension [see Warnings and Precautions (5.11)].

QTc Prolongation and Potential for Proarrhythmic Effects

Alert patients that ONAPGO may cause QTc prolongation and might produce proarrhythmic effects that could cause torsades de pointes and sudden death. Palpitations and syncope may signal the occurrence of an episode of torsades de pointes [see Warnings and Precautions (5.12)].

Priapism

Advise patients that ONAPGO may cause prolonged painful erections and that if this occurs, they should seek medical attention immediately [see Warnings and Precautions (5.15)]

ONAPGO Manufactured for: MDD US Operations, LLC, 9715 Key West Ave., Rockville, MD 20850.

MDD US Operations, LLC is a subsidiary of Supernus Pharmaceuticals, Inc.

ONAPGO is a trademark of BRITUSWIP LTD.

All trademarks are the property of their respective owners.

© 2025 MDD US Operations, LLC, a subsidiary of Supernus Pharmaceuticals Inc.

RA-ONG-V1

PATIENT INFORMATION
ONAPGO™ (on-AP-goh)
(apomorphine hydrochloride)
injection, for subcutaneous use

What is ONAPGO?

ONAPGO is a prescription medicine used to treat motor fluctuations (OFF episodes) in adults with advanced Parkinson's disease.

It is not known if ONAPGOis safe and effective in children.

Who should not use ONAPGO?

Do not use ONAPGO if you are:

- taking certain medicines called 5HT3 antagonists, including medicines to treat nausea (ondansetron, granisetron, dolasetron, palonosetron) and alosetron. People taking ondansetron together with apomorphine, the active ingredient in ONAPGO, have had very low blood pressure and lost consciousness (blacked out).
- allergic to apomorphine or to any of the ingredients in ONAPGO including sulfite. See the end of this Patient Information leaflet for a complete list of ingredients in ONAPGO. Sulfites can cause severe, life-threatening allergic reactions in some people. An allergy to sulfites is not the same as an allergy to sulfa. People with asthma are also more likely to be allergic to sulfites.
  Call your healthcare provider or get emergency help right away if you get any of the following symptoms of a severe life-threatening allergic reaction:

- hives
- itching

- rash
- swelling of the eyes, tongue, lips, or mouth

- chest pain
- throat tightness

- trouble breathing or swallowing

What should I tell my healthcare provider before using ONAPGO?

Before you start using ONAPGO, tell your healthcare provider about all of your medical conditions, including if you:

- have difficulty staying awake during the daytime.
- have dizziness.
- have fainting spells.
- have low blood pressure.
- have asthma.
- are allergic to any medicines containing sulfites.
- have heart problems.
- have had a stroke or other brain problems.
- have kidney problems.
- have liver problems.
- have a mental problem called a major psychotic disorder.
- drink alcohol.
- are pregnant or plan to become pregnant. It is not known if ONAPGO will harm your unborn baby.
- are breastfeeding or plan to breastfeed. It is not known if ONAPGO passes into your breast milk. You and your healthcare provider should decide if you will take ONAPGO or breastfeed.

Tell your healthcare provider about all the medicines you take, including prescription and non-prescription (over-the-counter) medicines, vitamins, and herbal supplements.

ONAPGO and certain other medicines may affect each other and how they work. Using ONAPGO with other medicines can cause serious side effects.

- If you take nitroglycerin under your tongue (sublingual) while using ONAPGO, your blood pressure may decrease and cause dizziness. If possible, you should lie down before taking nitroglycerin under your tongue, and then try to continue lying down for at least 45 minutes after you take nitroglycerin.

Know the medicines you take. Keep a list of them to show your healthcare provider or pharmacist when you get a new medicine.

How should I use ONAPGO?

- Read the Instructions for Use for specific information about the right way to use and to throw away (dispose of) ONAPGO.
- Use ONAPGO exactly as your healthcare provider tells you to use it.
- You will be taught the right way to use ONAPGO by your healthcare provider.
- Your healthcare provider will prescribe your dose of ONAPGO, and only they may change this dose if needed.
- Your healthcare provider or a nurse provided by the drug company will program your pump.
- Your healthcare provider will prescribe ONAPGO that comes in single-dose prefilled glass cartridges, that are used with the ONAPGO pump.
- Infuse ONAPGO under your skin (subcutaneously) only. Do not inject ONAPGO into a vein.
- Keep the infusion site clean, and change the infusion site every day.
- Use a new infusion set with each infusion. Never reuse an infusion set.
- ONAPGO is a clear and almost colorless liquid. Do not use ONAPGO if it looks cloudy, discolored, or contains particles.
- Your healthcare provider may prescribe trimethobenzamide to take while you are using ONAPGO, which is an antiemetic medicine to help decrease the symptoms of nausea and vomiting that can happen with ONAPGO.

What should I avoid while using ONAPGO?

- Do notdrink alcohol while you are using ONAPGO. It can increase your chance of developing serious side effects.
- Do nottake medicines that make you sleepy while you are using ONAPGO.
- Do notdrive, operate machinery, or do other dangerous activities until you know how ONAPGO affects you.
- Do notchange your body position too fast. Get up slowly from sitting or lying. ONAPGO can lower your blood pressure and cause dizziness or fainting.

What are the possible side effects of ONAPGO?

ONAPGO may cause serious side effects, including:

- blood clots.Infusing ONAPGO into a vein (intravenous) can cause blood clots. Do notinfuse ONAPGO in your vein.
- nausea and vomiting are common side effects.Nausea and vomiting, which may be serious or severe, can happen with ONAPGO. Your healthcare provider may prescribe medicine (trimethobenzamide) to help decrease nausea and vomiting. Follow your healthcare providers instructions on how to take and when to stop this medicine.
- sleepiness or falling asleep during the day is a common side effect and may be serious.Some people treated with ONAPGO may get sleepy during the day or fall asleep without warning while doing everyday activities such as talking, eating, or driving a car.
- dizziness is a common side effect and may be serious.ONAPGO can lower your blood pressure and cause dizziness. Dizziness can happen when ONAPGO treatment is started or when the ONAPGO dose is increased. Do notget up too fast from sitting or after lying down, especially if you have been sitting or lying down for a long period of time.
- falls.The changes that can happen with PD, and the effects of some PD medicines as well as the effects of trimethobenzamide, can increase the risk of falling. ONAPGO may also increase your risk of falling.
- infusion site reaction is a common side effect that may be serious.Infusion site reactions and infections including infusion site nodules, redness, bruising, swelling, rash, and itching may happen during treatment with ONAPGO.
- hallucinations or psychotic-like behavior.ONAPGO can cause or worsen psychotic-like behavior including hallucinations (seeing or hearing things that are not real), confusion, excessive suspicion, aggressive behavior, agitation, delusional beliefs (believing things that are not real), and disorganized thinking.
- sudden uncontrolled movements (dyskinesia) are a common side effect and may be serious.Some people with PD may get sudden, uncontrolled movements after treatment with some PD medicines. ONAPGO can cause or make dyskinesia worse.
- low red blood cells (hemolytic anemia).Tell your healthcare provider if you have any of the following signs or symptoms: you become pale, fast heartbeat, feel more tired or weaker than usual, skin or eyes look yellow, chest pain, shortness of breath or trouble breathing, dark-colored urine, fever, dizziness, or confusion.
- strong (intense) urges.Some people with PD have reported new or increased gambling urges, increased sexual urges, and other intense urges, while taking PD medicines, including ONAPGO.
- heart problems.If you have shortness of breath, fast heartbeat, or chest pain while taking ONAPGO, call your healthcare provider or get emergency help right away.
- serious heart rhythm changes (QT prolongation).Tell your healthcare provider right away if you have a change in your heartbeat (a fast or irregular heartbeat), or if you faint.
- allergic reaction.An allergic reaction can happen when using ONAPGO. Tell your healthcare provider or get medical help right away if you get any of these symptoms: hives, itching, rash, swelling of the eyes and tongue, or trouble breathing.
- tissue changes (fibrotic complications).Some people have had changes in the tissues of their pelvis, lungs, and heart valves when taking medicines called non-ergot derived dopamine agonists like ONAPGO.
- prolonged painful erections (priapism). ONAPGO may cause prolonged, painful erections in some people. If you have an erection that lasts more than 4 hours you should call your healthcare provider or go to the nearest hospital emergency room right away.

Other common side effects of ONAPGO include:

- headache
- trouble falling asleep or staying sleep (insomnia)

Tell your healthcare provider if you have any side effect that bothers you or that does not go away.

These are not all the possible side effects of ONAPGO. For more information, ask your healthcare provider or pharmacist.

Call your doctor for medical advice about side effects. You may report side effects to FDA at 1-800-FDA-1088.

How should I store ONAPGO?

- Store ONAPGO at room temperature between 68°F to 77°F (20°C to 25°C).

Keep ONAPGO and all medicines out of the reach of children.

General information about the safe and effective use of ONAPGO.

Medicines are sometimes prescribed for purposes other than those listed in a Patient Information leaflet. Do not use ONAPGO for a condition for which it was not prescribed. Do not give ONAPGO to other people, even if they have the same symptoms that you have. It may harm them.

You can ask your healthcare provider or pharmacist for information about ONAPGO that is written for health professionals.

What are the ingredients in ONAPGO?

Active ingredient:apomorphine hydrochloride

Inactive ingredients:hydrochloric acid, sodium metabisulfite in water for injection.

Manufactured for: MDD US Operations, LLC, 9715 Key West Ave., Rockville, MD 20850.

MDD US Operations, LLC is a subsidiary of Supernus Pharmaceuticals, Inc.

MDD US Operations, LLC is the exclusive licensee and distributor of ONAPGO in the United States and Its territories.

ONAPGO is a trademark of BRITUSWIP LTD.

©2025 MDD US Operations, LLC, a subsidiary of Supernus Pharmaceuticals, Inc.

For more information, go to ONAPGO.comor call 1-833-366-2746

This Patient Information has been approved by the U.S. Food and Drug Administration

Issued: 2/2025

RA-ONG-PPI-V1

Patient INSTRUCTIONS FOR USE ONAPGO™ (on-AP-goh)

This Instructions for Use contains information on how to use the ONAPGO Infusion System.

Please see the Important Safety Information, Full Prescribing Information, and Patient Information for ONAPGO.

MDD US Operations, LLC

Table of Contents
Table of Contents | 3
ONAPGO Infusion System | 5
Indication for Use | 5
Introduction to the Infusion System | 5
Important Information | 6
Pump Warnings and Precautions | 6
Pump Kit | 9
Pump Diagram | 9
Pump Screen Icons | 11
Other Supplies Provided Separately | 12
Storage | 13
Glass Drug Cartridge Storage | 13
Pump Storage | 13
Important Information You Need to Know Before Infusing ONAPGO | 13
Important Safety Information | 13
Check Pump Settings | 14
Step 1: Check Pump Settings | 14
Setup
Set Up the Pump | 23
Step 2: Wash Your Hands and Gather Supplies | 23
Step 3: Assemble Plastic Cartridge Holder | 25
Step 4: Prime the Infusion Line | 33
Prepare the Infusion Site | 38
Step 5: Select and Clean the Infusion Site | 38
Step 6: Connect the Cannula to the Body | 39
Connect the Infusion Line to Body | 40
Step 7: Connect the Infusion Line to the Cannula | 40
Start the Infusion | 41
Step 8: Start the Infusion | 41
Wear the Pump | 43
Step 9: Wear the Pump | 43
Reading the Pump Screen | 45
ON (Infusing Screen) | 45
Paused | 46
Primed | 46
Off | 46
Extra Dose / Pause / End
Give a + Dose (Extra Dose) | 51
Step 10: Give an Extra Dose | 51
Another Way of Giving an Extra Dose | 53
Understanding the Extra Dose Features | 54
Pause and Resume the Infusion | 55
Step 11: Pausing the Infusion | 55
Step 12: Resuming the Infusion | 57
Ending the Infusion | 59
Step 13: Ending the Infusion Early | 59
Step 14: Ending the Infusion Regularly | 64
Disconnecting in an Emergency | 68
Step 15: Disconnecting in an Emergency | 68
Pump Care
Disposal | 73
Glass Drug Cartridge, Plastic Cartridge Holder, and Infusion Line Disposal | 73
Pump Disposal | 73
Cleaning and Disinfecting the Pump | 74
Step 16: Clean and Disinfect the Pump | 75
Maintenance and Repair | 75
Replacing the Battery | 81
Step 17: Replacing the Battery | 81
Alarms & Errors
Alarms and Troubleshooting | 91
Error Codes | 91
Troubleshooting: If Your Infusion Line Did Not Prime | 98
Symbols Used on the ONAPGO Pump | 99
Technical characteristics of the Pump | 100
Electromagnetic Compatibility | 102
Tests of Accuracy | 104
Limited Warranty | 105
Contact & Support | 105

ONAPGO Infusion System

Indication for Use

The ONAPGO Infusion Pump is for the subcutaneous infusion of ONAPGO (apomorphine hydrochloride). ONAPGO is a prescription medicine used to treat motor fluctuations in adults with advanced Parkinson's disease (PD).

Only use the ONAPGO Infusion Pump if you have received instruction and training on how to correctly and safely use it. If you cannot use ONAPGO by yourself, contact your healthcare provider.

Only the accessories supplied by CANÈ S.p.A. (plastic cartridge holder and supplies provided in the infusion pump kit) may be used in conjunction with this pump. The pump must be set (programmed) by a trained healthcare provider or a trained nurse provided by the company (nurse navigator).

Introduction to the Infusion System

Below are common terms used throughout this Instructions for Use.

- Pump:controls the rate and amount of ONAPGO delivered to the body. It is programmed by a healthcare provider based on the patient's prescription. The pump displays the status of medicine delivery.
- Priming:refers to the task of removing all air from the infusion line (fluid pathway) before the infusion line is connected to the body.
- Flow Rate:the constant flow of ONAPGO given to the body over an extended period of time. The flow rate is expressed as milligrams per hour (mg/hr).
- Infusion Time:the total time that ONAPGO is infused per day.
- Extra Dose (+ Dose):a boost of ONAPGO (bolus dose) given over a short period of time in addition to the prescribed flow rate. Your healthcare provider will decide the number of extra doses that you could have each day. Your healthcare provider might prescribe an extra dose to be used as follows:
  - when you start the infusion each day, which can help the medicine work faster.
  - When you restart your medicine after not having it for 1 hour or more.
  - if you have an OFF episode during an infusion.
- Extra Dose (+ Dose) Lock:the amount of time before another extra dose can be given.
- Pump Settings:the patient's prescribed Flow Rate, Maximum Infusing Time Per Day, + Dose Quantity, + Dose Volume, and + Dose Lock. These settings can only be changed by a healthcare provider or clinical nurse navigator.

Important Information

- Read this entire Instructions for Use before using the infusion system.
  If any of the information is not clear, or if you have any questions, please contact Customer Support at 1-833-3ONAPGO (1-833-366-2746)
- Understanding how to use the pump and the potential alarms will help you avoid harm.
- You may hear motor noise when the pump is On and delivering ONAPGO. This noise is normal and means the pump is working correctly.
- The pump screen falls asleep (goes dark) after 30 seconds of inactivity. Press the UP ARROW button () to wake up the screen.

Pump Warnings and Precautions

Failure to follow the warnings and precautions below could cause return of your symptoms, damage to the pump, serious injury, or may lead to death in rare cases.

WARNINGS:

- Always check that the pump settings match the prescription before starting an infusion.
  See the Check Pump Settingssection on pages 14 to 18 for how to check the pump settings to make sure they are correct. If any of these settings do not match the prescription, contact your healthcare provider and/or clinical nurse navigator.
- The patient should receive no more than 98 mg of ONAPGO every 24 hours. This corresponds to one complete cartridge per day. Only use the pump with ONAPGO (apomorphine hydrochloride). ONAPGO comes in a glass cartridge that contains 98 mg/20 mL (4.9 mg/mL) of medicine. Only use the pump system within the temperatures on page 13 and other conditions for use in this Instructions for Use. Using the medicine and pump outside of these conditions may result in a system alarm.
- Only use the pump with the supplied plastic cartridge holder. Any other cartridge holder could damage the Pump and cause harm. Any non- approved cartridge holder voids warranty. MMD US Operations, LLC or its manufacturer is not responsible for any damages or injuries that happen if a different cartridge holder is used.
- Use the infusion set that is provided by your specialty pharmacy. The use of an inappropriate infusion set can cause loss or leakage of drug. Use a new infusion set at the beginning of every infusion. Ask your healthcare provider and/or clinical nurse navigator for more information.
- Do notprime the infusion line when it is connected to the body.
- Do notinsert the cannula into a blood vessel.
- If the medicine is cloudy, green, or contains particles, throw the glass drug Cartridge in a sharps container. (See the Disposalsection on page 73 for information on how to safely throw away ONAPGO). Get a new cartridge for your infusion.
- Clean the top of the glass drug cartridge with a new alcohol wipe before attaching the plastic cartridge holder.
- Always clean the selected infusion site with a new alcohol wipe. Make sure the site is dry before going on to the next step.
- Before starting your infusion, check for any leaks. Do notuse the pump if there are leaks. Contact Customer Support at 1-833-3ONAPGO (1-833-366-2746).
- Be careful when handling the Infusion Set to prevent needle sticks.
- Supplies included with your pump could pose a choking hazard for small children. Make sure that the pump and all supplies are kept away from small children.
- Supplies included with your pump (such as the infusion line) could pose a strangulation hazard. Arrange the infusion line to minimize the risk of strangulation. Make sure that these parts are stored in a secure place when not in use.
- Throw away (discard) the battery if it becomes damaged. Use a new, unopened battery.
  See Replacing the Batterysection on pages 81 to 85 (Steps 17.1 through 17.9) for instructions on how to replace the battery.
- The pump can detect a blockage in the line. If a partial blockage occurs, the pump will work the way it should until the line has a full blockage. An alarm will sound if the line has a full blockage.
- Be sure to disconnect the infusion line from the body before clearing a blockage alarm. If a blockage alarm is cleared while the infusion line is still attached, you may receive a small amount of additional medicine. See the Alarms and Troubleshootingsection on page 91.
- Confirm that the plastic cartridge holder and infusion line packaging are sealed and have not been damaged. If the packaging looks damaged, throw it away in a sharps container, and do not use it for your infusion. See the Disposalsection on page 73 for information on how to safely throw away ONAPGO. Use a new, undamaged product.
- If the battery becomes hot, do not continue with your infusion and call Customer Support at 1-833-3ONAPGO (1-833-366-2746).
- If your glass drug cartridge breaks while assembled in the plastic cartridge holder, do not separate it from the plastic cartridge holder. Disconnect the assembled cartridge from the pump and throw both away in a sharps container. See the Disposalsection on page 73 for information on how to safely throw away ONAPGO.
- Do notsnag or kink the infusion line while wearing the pump. Snagging or kinking the infusion line can cause a blockage (occlusion) or an interruption to the infusion.
- Always check the expiration date on the infusion set, plastic cartridge holder and glass drug cartridge prior to use. Do notuse expired materials.
- Do notuse expired or rechargeable batteries with the pump.
- If the glass drug cartridge is dropped, it should not be used and should be thrown away in a sharps container.
- If the pump gets wet, pause the infusion, disconnect the infusion line from the body, and store the pump in a dry place. This includes when swimming, showering, or excessively sweating.
- If your ONAPGO pump has expired, do not use it. Call your healthcare provider and/or clinical nurse navigator for a replacement of your ONAPGO pump.

PRECAUTIONS:

- Do notuse sharp objects to press the pump buttons. Only use your fingertips to press the pump buttons.
- Do notuse a damaged pump. If you have any concern about the correct functioning of the pump, or how to respond to an error, contact Customer Support at 1-833-3ONAPGO (1-833-366-2746).
- Read the infusion set Instructions for Use before using the infusion line.
- All pump settings, including sounds, are locked for your safety.
- Do notattempt to change the pump's prescribed settings. These can only be changed by a healthcare provider and/or clinical nurse navigator.
- Do notdisconnect the infusion line from the plastic cartridge holder while the pump is infusing.
- Only clean the infusion site with an alcohol wipe. Do not clean the infusion site with or apply disinfectants, perfumes, deodorants, or lotions to it.
- Free-flow is if gravity causes the drug to come out of the cartridge. The pump's pusher is made to have a secure connection with the rubber plunger in the cartridge to prevent free flow of the drug.

Pump Kit (Figure A)

Pump Diagram (Figures B, C, and D)

Figure B

Figure D

Figure C

All buttons will respond with a single press. If the screen is dark, press the UP ARROW button () to wake up the screen.

Item | Pump Feature | Description
a | Cartridge Connection | Area where assembled glass drug cartridge and plastic cartridge holder is attached to the pump.
b | Pump Pusher | Pushes ONAPGO from the glass drug cartridge into the infusion line.
c | Neck Lanyard Clips | Slots to clip on the lanyard.
d | LED | Lights up when an error cannot be displayed on the screen.
e | Screen | Where messages and menus appear.
f |  | +DOSE button gives an extra dose (+ dose) (if prescribed).
g |  | BACK button allows you to return to a previous screen, menu, or cancel an action.
h |  | MENU button allows you to access the menus.
i |  | OK button allows you to confirm menu selections or go on to the next value.
j |  | UP and DOWN ARROW buttons allow you to scroll through menus.
k | Battery Door | Door to access the battery.

Pump Screen Icons

The following table shows Icons that appear on the pump screen.

Icon | Name | Description
 | Back Arrow | The back arrow is shown when checking the pump settings. This icon is used to show that pressing the BACK button will return to a previous screen (Item 'g' in Figure B).
 | Caution | Caution is shown when an error or alarm is occurring.
 | Check Mark | A check mark is shown when the pump successfully completes a task.
 | Droplet | A blinking droplet is shown on the Infusing Screen when an infusion is on.
 | Dead Battery | The dead battery is shown when the pump battery is dead and must be replaced.
 | Low Battery | The Low Battery is shown when the pump battery is low and should be replaced before the next infusion.
 | OK Arrow | The OK Arrow is shown when checking the pump settings. This icon is used to show that pressing the OK button will confirm a selection or go on to the next value (Item 'i' in Figure B).
 | Padlock | Padlock is shown when the +Dose (extra dose) is not available.
 | Pause | Pause is shown when the infusion is paused.
 | +Dose (Extra Dose) | A +refers to the +Dose (extra dose) function.

Other Supplies Provided Separately

Additional supplies not in the pump kit include (Figure E):

Note:The plastic cartridge holder, glass drug cartridge and infusion set parts are sterile.

Figure E

Storage

Glass Drug Cartridge Storage

Store the glass drug cartridges at room temperature between 68°F to 77°F (20°C to 25°C). Store in original container.

Pump Storage

If the pump will not be used for 1 month or more, remove the battery. See Replacing the Batterysection on pages 81 to 85 (Steps 17.1 through 17.9) for instructions on how to remove the battery.

Store the pump in a dry place between -13°F to 158°F (-25°C to +70°C).

Keep the pump away from:

- Children and pets.
- Sources of heat or cold such as radiators, burners, stoves, freezer, or other heat or cold sources. Ask your healthcare provider or clinical nurse navigator if you are not sure.
- Direct sunlight.
- Strong electromagnetic fields such as magnets, speakers, mobile devices.
- Ionizing radiation, a type of device for radiotherapy or diagnostic radiology.
- Ultrasound devices.
- Magnetic Resonance Imaging (MRI) devices. The pump should not be used with an MRI.

If you are not sure about what to keep your pump away from, please contact your Customer Support at 1-833-3ONAPGO (1-833-366-2746).

Important Information You Need to Know Before Infusing ONAPGO

Important Safety Information

This Instructions for Use is for patients, caregivers, and healthcare providers or clinical nurse navigators and describes how to use the infusion system.

- The Instructions for Use are important for the safe and correct use of this infusion system.
- Read the entire Instructions for Use before using the infusion system.

Check Pump Settings

Step 1: Check Pump Settings

Confirm your pump settings match your prescription by doing the following steps.

Do notstart an infusion if any of the pump settings do not match your prescription. If this happens, contact your healthcare provider or clinical nurse navigator.

Step 1.1
Look at the pump.

If the pump screen is dark, press the Up Arrow button () to wake up the screen (Figure F).

Figure F

You will then see the Infusion Off screen (Figure G).

Figure G

Step 1.2

Press the MENU button () to find the pump settings (Figure H).

Figure H

Step 1.3

Highlight Settings on the screen using the DOWN ARROW button () (Figure I).

Figure I

Press the OK button () to begin reviewing the pump settings (Figure J).

Figure J

Step 1.4
Make sure the flow rate (mg/hr) matches your prescription (Figure K).

Figure K

Press the OK button () to move to the next screen (Figure L).

Figure L

Step 1.5
Make sure the infusion time (hr) matches your prescription (Figure M).

Figure M

Press the OK button () to move to the next screen (Figure N).

Figure N

Step 1.6
Make sure the number of +Doses/ Day (extra doses/day) matches your prescription (Figure O).

Figure O

Press the OK button () to move to the next screen (Figure P).

Figure P

Step 1.7
Make sure the +Dose (extra dose) amount (mg) matches your prescription (Figure Q).

Figure Q

Press the OK button () to move to next screen (Figure R).

Figure R

Step 1.8
Make sure +Dose Lock (extra dose lock) time (hr, min) matches your prescription (Figure S).

Figure S

Press the OK button () to move to next screen (Figure T).

Figure T

Step 1.9
You will see the software version (Figure U).

Figure U

Press the OK button () to move to the next screen (Figure V).

Figure V

Step 1.10
Exitwill be highlighted on the Menu screen (Figure W).

Figure W

Press the OK button () to exit the menu (Figure X).

Figure X

You will then see the Infusion Off screen (Figure Y). Set the pump aside on a clean surface and continue to the Set up the Pump section.

Figure Y

Setup
Within this section you will find:
Set up the Pump | 23
Prepare the Infusion Site | 38
Connect the Infusion Line to Body | 40
Start the Infusion | 41
Wear the Pump | 43
Reading the Pump Screen | 45

Set Up the Pump

Step 2: Wash Your Hands and Gather Supplies

Step 2.1
Go to a sink and wash your hands with soap and water, then dry your hands (Figure Z).

Figure Z

Step 2.2
Prepare a clean, flat surface such as a table to work on (Figure AA).

Figure AA

Step 2.3
Take the blue case and open it (Figure AB). Gather the additional supplies not included in the case (Figure AC).

Infusion System Kit Supplies Included in the Case (Figure AB):

- Pump Pouch
- Elastic Belt
- Pump
- Lanyard
- Spare Battery
- Battery Door Key

Additional Supplies not Included in the Case (Figure AC):

- Glass drug Cartridge (Sterile)
- Plastic Cartridge Holder (Sterile)
- Infusion Set parts (Sterile)
- Alcohol Wipes
- Towel (or Paper Towels)
- Sharps Container. See the DisposalSection on page 73 for information on how to safely throw away ONAPGO.

Do notuse other drug cartridges with the pump. The pump must only be used with an ONAPGO glass drug cartridge containing apomorphine hydrochloride 98 mg/20 mL (4.9mg/mL).

Do notuse other cartridge holders with the pump. The Pump must only be used with the plastic cartridge holder that is provided.

Step 3: Assemble Plastic Cartridge Holder

Step 3.1 Prepare Plastic Cartridge Holder
Look at the plastic cartridge holder package. Make sure the expiration date (EXP) has not passed (Figures AD and AE).

Figure AD

If the expiration date has passed:
Throw the plastic cartridge holder away in a sharps container and get a new plastic cartridge holder. See the Disposalsection on page 73 for information on how to safely throw away ONAPGO.

Figure AE

Remove the plastic cartridge holder from its package (Figure AF).

Figure AF

Step 3.2 Prepare Infusion Line
Look at the infusion line package. Make sure the expiration date has not passed (Figure AG).
If the expiration date has passed:
Throw the infusion line away in a sharps container and get a new infusion line. See the Disposalsection on page 73 for information on how to safely throw away ONAPGO.

Figure AG

Remove the infusion line from its package and tear off the paper tab.
Unravel the infusion line so it is straight (Figure AH).

Figure AH

Step 3.3 Connect Infusion Line and Plastic Cartridge Holder
Find the cartridge connector end of the infusion line (Figure AI).

Figure AI

Place the cartridge connector end of the infusion line over the tip of the plastic cartridge holder and turn the cartridge connector until it is snug (Figures AJ and AK).
Note:It only takes a small movement to secure the parts together.
Do not connect the infusion line to the body at this time.You must prime the infusion line before connecting it to your body.

Figure AJ

Figure AK

Step 3.4 Prepare Glass Drug Cartridge
Remove the glass drug cartridge from its carton and look at the label. Make sure the expiration date has not passed on the glass drug cartridge (Figures AL and AM).

Figure AL

If the expiration date has passed:
Throw the glass drug cartridge away in a sharps container and get a new glass drug cartridge. See the Disposalsection on page 73 for information on how to safely throw away ONAPGO.

Figure AM

Step 3.5 Check Medicine
Look at the glass drug cartridge. Make sure the liquid medicine inside the glass drug cartridge is clear, almost colorless, and free from particles (Figure AN).

Figure AN

Important Information

If the medicine is cloudy, discolored, or contains particles,throw away the glass drug cartridge in a sharps container and get a new one. See the Disposalsection on page 73 for information on how to safely throw away ONAPGO.

Step 3.6 Remove Flip Cap from Glass Drug Cartridge
Hold the glass drug cartridge and remove the flip cap (Figure AO). You may need to push hard to remove the flip cap.
You can throw the flip cap away in your household trash.

Figure AO

Step 3.7 Clean Glass Drug Cartridge
Clean the top of the glass drug cartridge with a new alcohol wipe (Figure AP).

Figure AP

Step 3.8 Place Glass Drug Cartridge
Place the glass drug cartridge on a flat surface on top of a towel or paper towel (Figure AQ).

Figure AQ

Step 3.9 Attach Plastic Cartridge Holder to Glass Drug Cartridge
Take the plastic cartridge holder. Place the plastic cartridge holder, with the infusion line attached, over the glass drug cartridge and push all the way down (Figures AR and AS).

Figure AR

Note:After letting go, the plastic cartridge holder may come up a bit so that it is not even with the bottom of the glass drug cartridge. This is normal.
A small amount of liquid medicine might come out of the glass drug cartridge. This is normal.
You have now created an "assembled cartridge" (Figure AT).
Note:Change the cartridge, cartridge holder, and administration set daily or between uses.
Note:If the infusion line is dropped or dirty, throw away (discard) the infusion line.
Warning:Do not puncture the cartridge with anything but the specified plastic cartridge holder.

Figure AS

Figure AT

Step 3.10 Place Assembled Cartridge on Pump
Hold the pump upright as shown (Figure AU).
Note:There are ridges at the bottom of the plastic cartridge Holder. You will use these ridges in the next step to align the assembled cartridge with the pump.

Figure AU

Take the assembled cartridge. Position the assembled cartridge above the pump with the ridges facing you (Figure AV).

Figure AV

Place the assembled cartridge onto the pump, as shown, with the ridges showing in the pump opening (Figure AW). The assembled cartridge should sit flush against the pump with no gap.

Figure AW

Step 3.11 Attach Assembled Cartridge to Pump
Push downthe assembled cartridge firmly and twistuntil you feel it lock into place and the ridges are no longer showing (Figure AX).

Figure AX

Look at the Pump opening.

- If you only see a smooth surface with no gap between the assembled cartridge and the pump, then the assembled cartridge is correctly attached (Figure AY) and you can continue to Step 4.
- If you see any portion of the ridges in the space (Figure AZ), then push down firmly again as you twist the assembled cartridge until the ridges are no longer showing (Figure AY).

Figure AY
Figure AZ

Step 4: Prime the Infusion Line

Priming the infusion line (Figure BA) pushes liquid through the system to remove all air from the glass drug cartridge and infusion line. All air must be removed from the system before the infusion line is connected to the infusion site on the body.

Read the Instructions for Use for the infusion set before using the infusion line.

Do notprime the infusion line when it is connected to the infusion site on the body.

Step 4.1
Take the site connector end of the infusion line and place it on a towel (Figure BB).

Figure BB

Step 4.2
Take the pump. Press the UP ARROW button () to wake up the screen (Figure BC).

Figure BC

You will then see the Infusion Off screen (Figure BD).

Figure BD

Step 4.3
Press the MENU button () to enter the pump menu (Figure BE).

Figure BE

Step 4.4
The Primeoption will be highlighted on the Menu screen (Figure BF).

Figure BF

Press the OK button () to continue (Figure BG).

Figure BG

Step 4.5
You will see the Ready to Prime screen (Figure BH).

Figure BH

Press the OK button () to prime the infusion line (Figure BI).
Note:Make sure that the site connector is held over the towel and not attached to the body. During priming, you will be looking for drops to come out of the site connector.

Figure BI

You will then see the Priming screen flashing (Figure BJ). This means that the pump is priming.

Figure BJ

During Priming…
Check the connector end of the infusion line for drops of liquid medicine (Figure BK).

Figure BK

Important Information

Do notallow the medicine to come into contact with your clothing, carpeting, or furniture, as it can stain.

Step 4.6
When priming is done you will see this screen (Figure BL).

Figure BL

After priming…
Check that all air gaps or large air bubbles are removed from the line (Figure BM).

Figure BM

Press the OK button () for menu options (Figure BN).

Figure BN

Step 4.7
Did you see drops and confirm no large air bubbles or gaps in the line?

- If Yes, Press OK button () to Continue (Figures BO and BP).
- If No, Highlight Repeat Primeon the screen using the DOWN ARROW button ().
  Then press the OK button () to prime again.
  If after two priming attempts the line is still not primed, see page 98 for troubleshooting information.

Figure BO
Figure BP

Step 4.8
You will see a screen that says Wait! Connect Line to Body (Figure BQ).

Figure BQ

Put down the pump(Figure BR) and follow the next sections to "Prepare the Infusion Site" and "Connect the Infusion Line to Body".

Figure BR

Prepare the Infusion Site

You will insert the cannula (a small tube that allows the medicine to be delivered) into the selected infusion site.

Step 5: Select and Clean the Infusion Site

Step 5.1
Select one of the following infusion sites (see blue shaded areas in Figure BS):

- Lower stomach (Abdomen), at least 2 inches away from belly button
- Top of thigh
- Lower back
- Upper back (only to be used when a caregiver or healthcare provider is preparing the infusion).

Figure BS

Important Information

Change the infusion site every day (rotate sites) to avoid skin-related problems, such as bumps or nodules.

Do notselect an infusion site that is bruised, has bumps or nodules, or is irritated.

Do notselect an infusion site other than those listed and shown in Figure BS.

Step 5.2
Get an alcohol wipe. Clean the selected infusion site with a new alcohol wipe (Figure BT).
Make sure the area is dry before moving on to Step 6.

Figure BT

Note:If the infusion line is dropped or dirty, throw away (discard) the infusion line.

Step 6: Connect the Cannula to the Body

Step 6.1
Following the infusion set Instructions for Use, insert the cannula into the cleaned infusion site (Figure BU).

Figure BU

Read the Instructions for Use for the infusion set before using the infusion line.

Do notinsert the cannula into a blood vessel.

Do notinsert the cannula into a bump or nodule, as it can result in a blockage (occlusion).

Connect the Infusion Line to Body

Step 7: Connect the Infusion Line to the Cannula

Step 7.1
Take the site connector end of the infusion line. Pinch the sides of it and pull on the end of the site connector to open it (Figure BV).

Figure BV

Step 7.2
Connect the primed infusion line to the cannula on the body by placing the site connector over the cannula and then closing it (Figures BW and BX). For more information, follow the Instructions for Use provided with the infusion set.

Figure BW
Figure BX

Start the Infusion

Step 8: Start the Infusion

Step 8.1
Pick up the pump.

Press the UP ARROW button () to wake up the screen (Figure BY).

Figure BY

You will see a screen that says Connect Line to Body (Figure BZ).

Figure BZ

Now that you have connected the line to your body, press the OK button () (Figure CA).

Figure CA

You will see a screen that says Confirm Line Connected (Figure CB).

Figure CB

Make sure that the site connector is attached to the body.
Then press the OK button () (Figure CC).

Figure CC

Step 8.2
You will see a screen that says Start Infusion (Figure CD).

Figure CD

When ready, press the OK button () to start the infusion (Figure CE).

Figure CE

You will then see the Infusion Started screen. The checkmark at the bottom of the screen means that the infusion has successfully started (Figure CF).

Figure CF

After the infusion has started, you will see the Infusing Screen. The flashing droplet means that the pump is now infusing (Figure CG). Next to the droplet, you will also see the amount of time before the infusion ends.

Figure CG

Wear the Pump

Step 9: Wear the Pump

You must place the pump inside the pump pouch and then attach it to either the elastic belt or the lanyard, whichever you prefer.
Using the Elastic Belt

Take the elastic belt and pump pouch. Insert the elastic belt into the loop on the back of the pump pouch (Figure CH).

Figure CH

Take the pump. Place the pump inside of the pump pouch (Figure CI).

Figure CI

Secure the elastic belt around the waist (Figure CJ).

Figure CJ

Do notsnag or kink the infusion line while wearing the pump. Snagging or kinking the infusion line can cause a blockage (occlusion) or an interruption to the infusion.

Using the Neck Lanyard

Take the neck lanyard and pump. Hook the lanyard to the neck lanyard Clips (Figure CK) located on the pump.

Figure CK

Take the pump pouch. Place the pump inside of the pump pouch (Figure CL).

Figure CL

Place the lanyard around patient's neck (Figure CM).

Figure CM

Do notsnag or kink the infusion line while wearing the Pump. Snagging or kinking the infusion line can cause a blockage (occlusion) or an interruption to the infusion.

Reading the Pump Screen

There are 4 main modes for the pump: On (Infusing Screen), Paused, Primed, and Infusion Off. Each mode is described below.

ON (Infusing Screen)

When the pump is On, and the infusion is running, the following icons and information will be seen (Figure CN):

Figure CN

When the pump is On and you attempt to give an extra dose (+Dose), the following icon will be seen when the extra dose (+Dose) is locked out (Figure CO):

Figure CO

Paused

When the infusion is paused, the following screen will be seen (Figure CP):

Figure CP

To pause the infusion, see the Pausing the Infusioninstructions on page 55.

Primed

When the pump is primed, but the infusion has not started, the following screen will be seen (Figure CQ):

Figure CQ

OFF

When the pump is not infusing, the following screen will be seen (Figure CR):

Figure CR

+ Dose / Pause / End
Within this section you will find:
Give a +Dose | 51
Pause and Resume the Infusion | 55
Ending the Infusion | 59
Disconnecting in an Emergency | 68

Give a +Dose (Extra Dose)

Step 10: Give an Extra Dose (+ Dose)

An extra dose (+Dose) is only available if it has been prescribed by the healthcare provider. If an extra dose (+Dose) has NOT been prescribed, skip this section.

Note:An extra dose (+Dose) can only be given after the pump has been primed and while the pump is infusing.

Step 10.1
Take the pump. Press the UP ARROW button () to wake up the screen (Figure CS).

Figure CS

Step 10.2
Press the +Dose button () (Figure CT).

Figure CT

You will then see the +Dose screen. Press the DOWN ARROW button () to highlight Yes(Figure CU).

Figure CU

Step 10.3
Press the OK button () to continue (Figure CV).

Figure CV

The pump will now give the extra dose (+Dose) (Figure CW).

Figure CW

When the extra dose is delivered, you will then see the +Dose Delivered screen with a check mark on the bottom (Figure CX).

Figure CX

The pump will then automatically go back to the Infusing screen (Figure CY).
Note:Administer extra doses (+Doses) at least 3 hours apart. Administer no more than 3 extra doses a day.

Figure CY

Another Way of Giving an Extra Dose (+ Dose)

Do notrepeat the steps below if you have already given an extra dose using the +Dose button ().

Take the pump.
Press the menu button () (Figure CZ).

Figure CZ

Use the DOWN ARROW button () to highlight Give +Dose (Figure DA).

Figure DA

Press the OK button () to continue (Figure DB).

Figure DB

You will then see the +Dose screen.
Press the DOWN ARROW button () to highlight Yes (Figure DC)

Figure DC

Press the OK button () to deliver the extra dose (+Dose)(Figure DD).

Figure DD

Understanding the Extra Dose (+ Dose) Features

If you see the +Dose Locked icon (Figure DE) on the home screen, it means that an extra dose is not allowed.
This is because the minimum amount of time has not passed since the last extra dose (+Dose) was given.
The time between allowable extra doses (+Doses) is prescribed by the healthcare provider.

Figure DE

When the +Dose is locked, you can see the amount of time remaining before another extra dose (+Dose) can be given, by pressing the +Dose button () (Figure DF).

Figure DF

If you see the +Dose None Remaining message (Figure DG), it means the maximum number of extra doses has been reached and none remain for that infusion.

Figure DG

Pause and Resume the Infusion

If the pump is at risk for getting wet, pause the infusion, disconnect the infusion line from the body, and store the pump in a dry place. This includes swimming, showering, or excessive sweating.

Step 11: Pausing the Infusion

Step 11.1
Take the pump. Press the UP ARROW button () to wake up the screen (Figure DH).

Figure DH

Step 11.2
Press the MENU button () to enter the pump menu (Figure DI).

Figure DI

Step 11.3
Pause option will be highlighted on the Menu screen (Figure DJ).

Figure DJ

Step 11.4
Press the OK button () to pause the infusion (Figure DK).

Figure DK

You will then see the Paused screen (Figure DL).

Figure DL

Step 11.5 (If Needed)
If needed, remove the infusion line from your body (Figure DM) while leaving cannula on your skin. There is no need to cover the site connector once removed, as it is self-sealing.

Figure DM

Step 12: Resuming the Infusion

Step 12.1 (If Needed)
Take the site connector end of the infusion line. Reattach the infusion line to the infusion site (Figure DN).

Figure DN

Step 12.2
Take the pump. Press the UP ARROW button () to wake up the screen (Figure DO).

Figure DO
�

Step 12.3
Press the MENU button () to enter the pump menu (Figure DP).

Figure DP

Step 12.4
Resume option will be highlighted on the Menu screen (Figure DQ).

Figure DQ

Step 12.5
Press the OK button () to resume the infusion (Figure DR).

Figure DR

You will then see the Infusion Resumed screen with a check mark on the bottom (Figure DS).

Figure DS

The pump will automatically return to the Infusing Screen (Figure DT).

Figure DT

Ending the Infusion

The infusion will run for the programmed amount of time, or it can be ended early.

Step 13: Ending the Infusion Early

Step 13.1
Take the pump. Press the UP ARROW button () to wake up the screen (Figure DU).

Figure DU

Step 13.2
Press the MENU button () to enter the pump menu (Figure DV).

Figure DV

Step 13.3
Press the DOWN ARROW button () to highlight End(Figure DW).

Figure DW

Press the OK button () to end the infusion (Figure DX).

Figure DX

Step 13.4
Press the DOWN ARROW button () to highlight Yes(Figure DY).

Figure DY

Press the OK button () to select Yes(Figure DZ).

Figure DZ

You will then see the Stop! Remove Line From Body screen (Figure EA).
Do notpress the OK button at this time.

Figure EA

Step 13.5
Remove the infusion line from the body (Figure EB).

Figure EB

Step 13.6
Press the OK button () to confirm that the infusion line has been removed from the body (Figure EC).

Figure EC

You will then see the Ending Infusion screen, indicating the ending of the infusion (Figure ED). It may take several minutes to retract the pusher and end the infusion.

Figure ED

When the pump has ended the infusion, you will see the Infusion Off screen (Figure EE).

Figure EE

Note:If you press the back () button as the infusion is ending, the pusher reset will pause. Press the OK button () to resume ending the infusion and resetting the pusher.

Step 13.7
Remove the cannula from the body (Figure EF).

Figure EF

Step 13.8
Take a new alcohol wipe. Clean the infusion site with a new alcohol wipe (Figure EG).

Figure EG

Step 13.9
Gently massage the area of the infusion site to break up any excess fluid buildup. This will help prevent skin nodules or bumps and irritations (Figure EH).

Figure EH

Step 13.10
Take the pump. Twist the assembled cartridge to the left (counterclockwise) and lift it straight up to remove the plastic cartridge holder, glass drug cartridge, and infusion line altogether (Figure EI).

Figure EI

Do notseparate the infusion line or the glass drug cartridge from the plastic cartridge holder.

Note:If the plastic cartridge holder detaches from the glass drug cartridge when removing, continue to remove the plastic cartridge holder. Set aside the plastic cartridge holder and remove the glass drug cartridge by pulling it up and off the pump. Continue to Step 13.11.

Step 13.11
Throw away the used Infusion line, glass drug cartridge, plastic cartridge holder, and cannula into a sharps container right away after use (Figure EJ).
Do notthrow away (dispose of) the infusion line, glass drug cartridge, or plastic cartridge holder in your household trash.
See the Disposalsection on page 73 for information on how to safely throw away ONAPGO.

Figure EJ

Visually Check the Pump
Right after you use the pump, look it over (visually check) to see if you notice any soiling on the pump.
Wipe off any soiling that you see with isopropyl alcohol. (See the Clean and Disinfect the Pumpsection on page 74.)

Step 14: Ending the Infusion Regularly

Step 14.1
At 1 hour, 10 minutes, and 5 minutes remaining in the infusion, the pump will give a reminder on the screen and you will hear occasional beeping (Figure EK).

Figure EK

You must press the OK button () to dismiss the message (Figure EL).
Note:The 10-minute remaining screen is shown in Figure EK as an example.

Figure EL

Step 14.2
When the infusion ends, the Ended screen will appear with 0 minutes remaining (Figure EM) and you will hear a beep.

Figure EM

Press the OK button () to select Yes(Figure EN).

Figure EN

Step 14.3
You will then see the Stop! Remove Line From Body screen (Figure EO).
Do notpress the OK button at this time.

Figure EO

Step 14.4
Remove infusion line from the body (Figure EP).

Figure EP

The infusion line must be removed from the infusion site before pressing the OK button.

Step 14.5
Take the pump.
Press the OK button () to confirm that the infusion line has been removed from the body (Figure EQ).

Figure EQ

The pump will begin to reset, and you will see the Ending Infusion screen (Figure ER). It may take several minutes to retract the pusher and end the infusion.

Figure ER

Next, you will see the Infusion Off screen (Figure ES).

Figure ES

Note:If you press the back () button as the infusion is ending, the pusher reset will pause. Press the OK button () to resume ending the infusion and resetting the pusher.

Step 14.6
Remove the cannula from the body (Figure ET).

Figure ET

Step 14.7
Take a new alcohol wipe. Clean the infusion site with a new alcohol wipe (Figure EU).

Figure EU

Step 14.8
Gently massage the area of the infusion site to break up any excess fluid buildup. This will help prevent skin bumps or nodules and irritations (Figure EV).

Figure EV

Step 14.9
Take the pump. Twist the plastic cartridge holder to the left (counterclockwise) and lift it straight up to remove the plastic cartridge holder, glass drug cartridge, and infusion line (Figure EW).

Figure EW

Do notseparate the infusion line or the glass drug cartridge from the plastic cartridge holder.

Note:If the plastic cartridge holder detaches from the glass drug cartridge when removing, continue to remove the plastic cartridge holder. Set aside the plastic cartridge holder and remove the glass drug cartridge by pulling it up and off the pump. Continue to Step 14.10.

Step 14.10
Put the used infusion line, glass drug cartridge, plastic cartridge holder, and cannula into a sharps container right away after use (Figure EX).
Do notthrow away (dispose of) the infusion line, glass drug cartridge, or plastic cartridge holder in your household trash.
See the Disposalsection on page 73 for information on how to safely throw away ONAPGO.

Figure EX

Visually Check the Pump
Right after you use the pump, look it over (visually check) to see if you notice any soiling.
Wipe off any soiling that you see with isopropyl alcohol. (See the Clean and Disinfect the pumpsection on page 74.)

Disconnecting in an Emergency

If you are having a medical emergency, follow the steps below to disconnect from the pump.

Step 15: Disconnecting in an Emergency

Step 15.1
In the United States, dial 9-1-1 from any telephone for immediate medical assistance (Figure EY).

Figure EY

Step 15.2
Remove the infusion line from your body (Figure EZ).

Figure EZ

Step 15.3
Follow the Ending the Infusion Earlyinstructions on pages 59 to 63.

Pump Care
Within this section you will find:
Disposal | 73
Cleaning and Disinfecting the Pump | 74
Replacing the Battery | 81

Disposal

Glass Drug Cartridge, Plastic Cartridge Holder, and Infusion Line Disposal

- After the infusion, put the combined glass drug cartridge, plastic cartridge holder, and infusion set into a sharps container right away after use (Figure FA).
  Do notthrow away (dispose of) the glass drug cartridge, plastic cartridge holder, or infusion set in your household trash.
  Do notseparate the parts.
- If you do not have an FDA-cleared sharps container, you may use a household container that is:
  - Made of a heavy-duty plastic.
  - Can be closed with a tight-fitting, puncture-resistant lid.
  - Upright and stable during use.
  - Leak resistant.
  - Properly labeled to warn of hazardous waste inside the container.
- When your sharps container is almost full, you will need to follow your community guidelines for the right way to dispose of your sharps container. There may be state or local laws about how you should throw away used needles.
- For more information about safe sharps disposal, and for specific information about sharps disposal in the state that you live in, go to the FDA's website at: http://www.fda.gov/safesharpsdisposal.
- Do notdispose of your used sharps container in household trash unless your community guidelines permit this.
- Do notrecycle your used sharps container.

Figure FA

Pump Disposal

At the end of the expected life of the pump, contact Customer Support at 1-833-3ONAPGO (1-833-366-2746) for information and instructions about safe pump disposal.

Cleaning and Disinfecting the Pump

The Pump is a reusable device and should be cleaned and disinfected whenever you see any traces of dirt.

Follow the instructions below and on the following pages for cleaning and disinfecting the pump.

Do notclean and disinfect the pump if it is missing any parts (e.g., battery compartment door) or if you see damage to the front label.

The pump is not waterproof. Do notimmerse the pump in liquid.

Do notplace the pump under running water.

Do notget any liquid inside of the pump. If the pump becomes wet, dry it right away.

When cleaning the pump, dry your hands oftento avoid the build-up of liquid on the pump surface.

Do notclean the pump with bleach or harsh (abrasive) detergents.

Do notsterilize the pump.

Do notclean the pump in a dishwasher.

Do notdry the pump in a microwave.

Step 16: Clean and Disinfect the Pump

Always carefully follow the steps below when cleaning and disinfecting the pump.

Step 16.1 Preparing to Clean the Pump

Wash and Dry Your Hands
Wash your hands with soap and water, then dry your hands (Figure FB).

Figure FB

Set up a Clean Work Area
Set up a clean work area on a clean flat surface (Figure FC).

Figure FC

Gather Supplies
Gather the following supplies (available at most supermarkets or pharmacies) (Figure FD):

- Neutral detergent
- Isopropyl alcohol, 70% (rubbing alcohol)
- Purified or distilled water
- Toothbrush with soft bristles
- Several pieces of gauze (at least 8)

Optional Supplies:

- Disposable gloves (to be used during cleaning)
- Disposable cups (to hold water and detergent)
- Absorbent towel (to keep on the table and dry your hands)

Note:If you have difficulty finding the supplies to clean your Pump, contact your Specialty Pharmacy or Customer Support at 1-833-3ONAPGO (1-833-366-2746).

Figure FD

Do notreuse the disposable gauze when cleaning the Pump. Throw away each piece of gauze after use.
Make sure to follow the instructions provided by the manufacturers of the detergent and the isopropyl alcohol.

Step 16.2 Thoroughly Clean the Pump with the Toothbrush

Always clean and disinfect the toothbrush each time you clean the pump, or use a new toothbrush each time you clean the pump. Replace the toothbrush if the bristles get worn or dirty.

Wet the Toothbrush
Use the purified or distilled water to slightly moisten the bristles of the toothbrush.

Add a Drop of Detergent
Add a drop of detergent to the toothbrush.
Brush Gently Until Clean
Use the toothbrush head to gently brush any areas of the pump that are dirty (Figure FE) until you see the pump is clean.

Figure FE

Do notvigorously scrub the pump with the toothbrush.

Step 16.3 Dry the Pump

Wipe Dry with Gauze
Wipe all areas of the pump with a new dry gauze, to remove excess detergent residue or moisture (Figure FF), then throw away the gauze.
Visually Check the Pump
Visually check that all dirt and residue has been removed.

Figure FF

Step 16.4 Thoroughly Clean the Pump with Gauze

Dampen a Gauze with Detergent andWater
Dampen a new gauze with detergent and purified or distilled water.
Wipe the Pump with Gauze
Wipe the outer surfaces of the pump using the dampened gauze (Figure FG), then throw away the gauze.

Figure FG

16.5 Dampen a New Gauze with Water
Dampen a new gauze with purified or distilled water.
16.6 Wipe the Pump with Gauze
Wipe the outer surfaces of the pump with the dampened gauze to remove any detergent residue (Figure FH), then throw away the gauze.

Figure FH

Step 16.7 Dry the Pump

Wipe Dry with Gauze
Dry all areas of the pump with a new dry gauze (Figure FI), then throw away the gauze.

Figure FI

Visually Check the Pump
Visually check the pump for any soiling. Repeat the cleaning process if you see any traces of soiling.

Step 16.8 Disinfect the Pump with 70% Isopropyl Alcohol

Soak a Gauze with Alcohol
Soak a new gauze with 70% isopropyl alcohol.
Wipe Pump with Gauze for at least 1 Minute
Wipe the outer surfaces of the pump using the soaked gauze for at least one minute(Figure FJ), then throw away the gauze.

Figure FJ

Do notimmerse the pump in isopropyl alcohol.

Step 16.9 Let Pump Air Dry

Let Pump Air Dry for at least 5 Minutes
Set the pump aside on a clean dry surface and let the pump air dry for at least 5 minutes(Figure FK).

Figure FK

The isopropyl alcohol must be in contact with the device surfaces for at least 5 minutesto disinfect the pump.

Step 16.10 Disinfect the Pump with 70% Isopropyl Alcohol

Soak a Gauze with Alcohol
Soak a new gauze with 70% isopropyl alcohol.
Wipe Pump with Gauze again for at least 1 Minute
Wipe the outer surfaces of the pump using the soaked gauze for at least one minute(Figure FL), then throw away the gauze.

Figure FL

Do notimmerse the pump in isopropyl alcohol.

Step 16.11 Let Pump Air Dry

Let Pump Air Dry for at least 5 Minutes
Set the pump aside on a clean dry surface and let the pump air dry for at least 5 minutes(Figure FM).

Figure FM

Make sure Pump is Dry
Make sure the pump is completely dry, and all the isopropyl alcohol has evaporated.

The isopropyl alcohol must be in contact with the device surfaces for at least 5 minutesto disinfect the pump.

Step 16.12 Use Water to Remove Alcohol Residue

Dampen Gauze with Water
Dampen a new gauze with purified or distilled water.

Figure FN

Wipe the Pump with Gauze
Wipe the outer surfaces of the pump with the dampened gauze to remove any disinfectant residue (Figure FN), then throw away the gauze.

Step 16.13 Dry the Pump

Wipe Dry with Gauze
Dry all areas of the pump with a new dry gauze (Figure FO), then throw away the gauze.
Visually Check the Pump
Visually inspect the pump to make sure it is clean.

Figure FO

If you see any traces of dirt, repeat the entire cleaning and disinfecting procedure.

If the pump has not been cleaned for a long period of time, some stains caused by the liquid medicine may not come off during the cleaning and disinfecting process.

Maintenance and Repair

If the pump is used correctly as outlined in this Instructions for Use, the pump does not need programmed service maintenance from the manufacturer (CANÈ S.p.A. Medical Technology Company).

If the pump stops working, is damaged, or shows a numbered error code, contact your Specialty Pharmacyor Customer Support at 1-833-3ONAPGO (1-833-366-2746).

Replacing the Battery

Always have a replacement lithium CR 123A battery available for use.

Do notreplace the battery while the Infusion Line is connected to your body or during an active infusion as this could cause harm.

Do notuse a battery other than lithium CR 123A.

Do notuse expired or rechargeable batteries with the Pump.

Step 17: Replacing the Battery

To replace the battery, follow these steps:

Step 17.1
You should see the Infusion Off screen (Figure FP).

Figure FP

Step 17.2
Take a new 3 volt lithium battery (model CR 123A) (Figure FQ) and the battery door key (Figure FR).

Figure FQ
Figure FR

Step 17.3
Take the battery door key and pump. Insert the battery door key into the battery door keyhole on the bottom of the pump (Figure FS).

Figure FS

Push the battery door key away from the pump (Figure FT) to open the battery door.

Figure FT

Step 17.4
Pull the battery door up and all the way out so that the ribbon attached to the battery door pops out the battery (Figure FU).

Figure FU

Do notuse any other object to remove the battery.

If the battery does not pop out:

Hold the pump and the battery door firmly in one hand (Figure FV) and

Figure FV

Strike the palm of your other hand with the pump, to jolt the battery from the compartment (Figure FW).

Figure FW

Step 17.5
Throw away the expired battery per local guidelines (Figure FX).

Figure FX

Step 17.6
Wait 10 seconds before inserting a new battery (Figure FY). This allows the pump to reset.

Figure FY

Step 17.7
Take your new, unopened 3 volt lithium battery, model CR 123A (Figure FZ).
Open the package.

Figure FZ

Step 17.8
Take the pump. Insert the new battery by placing it on top of the ribbon with the negative end (-) of the battery towards the silver side of the pump where the plastic cartridge holder is attached, and the positive end (+) towards the flat end of the pump (Figure GA).
Note:The battery should be placed on top of the ribbon to help with future removal and replacement.

Figure GA

Step 17.9

Close the battery door by pushing it back into place (Figure GB).

Figure GB

You will hear a series of beeps when the new battery is fully inserted (Figure GC).

Figure GC

The pump screen will wake up and show the logo screen followed by the Infusion Off screen (Figure GD).

Figure GD

Alarms & Errors

Within this section you will find:

Error Codes

91

Troubleshooting

98

Alarms and Troubleshooting

Error Codes

An error code will display on the screen if there is something wrong with the pump. You will hear a beep when there is an error code, and the LED next to the screen may light up. The table below gives an overview of the possible error codes that may happen, what they mean, and what to do to fix them.

If the corrective actions provided below do not fix the issue, contact Customer Support at 1-833-3ONAPGO (1-833-366-2746).

Do nottry to start or continue with your infusion when the screen displays an error. This will help avoid overdose or underdose.

Blank Screen Error
If a Blank Screen Error occurs, follow the steps below.
Figure GE | What is happening? | You will hear intermittent beeps. The screen is blank and the LED lights up (Figure GE).
Figure GE | What does it mean? | The pump has detected an error that needs to be addressed.
Figure GE | What to do? | Contact Customer Support at 1-833-3ONAPGO (1-833-366-2746).

Error 2
If Error 2 occurs, follow the steps below.
Figure GF Figure GG | What is happening? | You will hear a continuous tone and the screen will stay on and show a notification (Figure GF) until the error is addressed.
Figure GF Figure GG | What does it mean? | The pump has detected an error that needs to be addressed.
Figure GF Figure GG | What to do? | 1. Press the OK button () to clear the error (Figure GF). The pump will try to fix itself. 2. If the error clears, you can continue with your infusion as normal. 3. If the error message remains, contact Customer Support at 1-833-3ONAPGO (1-833-366-2746). (Figure GG).

Error 3, Error 5, Error 7
If Error 3, Error 5, or Error 7 occurs, follow the steps below.
Figure GH Figure GI | What is happening? | You will hear intermittent beeps. The screen will show a notification (Figure GH) and the LED may light up.
Figure GH Figure GI | What does it mean? | The pump has detected an error that needs to be addressed.
Figure GH Figure GI | What to do? | 1. Press the OK button () to clear the error (Figure GH). The pump will try to fix itself. 2. If the error clears, you can continue with your infusion as normal. 3. If the error message remains, contact Customer Support at 1-833-3ONAPGO (1-833-366-2746) (Figure GI).

Error 4
If Error 4 occurs, follow the steps below.
Figure GJ | What is happening? | You will hear intermittent beeps and the screen will stay on and show a notification (Figure GJ) until the error is addressed.
Figure GJ | What does it mean? | The pump has detected an error that needs to be addressed.
Figure GJ | What to do? | Contact Customer Support at 1-833-3ONAPGO (1-833-366-2746) (Figure GJ).

Error 6, Error 8, Error 9, Error 11
If Error 6, Error 8, Error 9, or Error 11 occurs, follow the steps below.
*Note: Images below show Error 6 as an example. Figure GK Figure GL | What is happening? | You will hear intermittent beeps and the screen will stay on and show a notification (Figure GK) until the error is addressed.
*Note: Images below show Error 6 as an example. Figure GK Figure GL | What does it mean? | The pump has detected an error that needs to be addressed.
*Note: Images below show Error 6 as an example. Figure GK Figure GL | What to do? | 1. If attached to the body, remove the infusion line. 2. Press the OK button () to clear the error (Figure GK). The pump will try to fix itself. 3. If the error clears, you can continue with your infusion as normal. 4. If the error message remains, contact your healthcare provider orclinical nurse navigator (Figure GL).

Blockage
If the Blockage Error occurs, follow the steps below.
Figure GM Figure GN Figure GO Figure GP | What is happening? | You will hear intermittent beeps and the screen will stay on and show a notification (Figure GM) until the error is addressed.
Figure GM Figure GN Figure GO Figure GP | What does it mean? | Too much pressure has been detected in the Infusion Line. Something may be blocking the infusion flow.
Figure GM Figure GN Figure GO Figure GP | What to do? | 1. If attached to the body, remove the infusion line site connector from your body while leaving the cannula connected to your skin (Figure GM). Press the OK button (). 2. Straighten the infusion line out completely to remove any kinks from the line. 3. Make sure the infusion line site connector end is over a sink or a towel before pressing the OK button. After the blockage is cleared, some drug may come out. 4. Press the OK button () to clear the error (Figure GN). The pump will try to fix itself. 5. If the blockage is cleared, the infusion will continue. Reattach the infusion line to your body and press the OK button () (Figure GO). 6. If the error message remains, Contact your healthcare provider or clinical nurse navigator (Figure GP).
Warning:If something is blocking the infusion of ONAPGO, such as a kink, be sure to disconnect the infusion line before clearing the blockage alarm. If the infusion line is attached to the body when the error is cleared, you may receive a small additional amount of medicine.

Low Battery
If the Low Battery Alert occurs, follow the steps below.
Figure GQ Figure GR | What is happening? | You will hear a beep and see a notification (Figure GQ or Figure GR) on the screen.
Figure GQ Figure GR | What does it mean? | The battery is getting low.
Figure GQ Figure GR | What to do? | During an Infusion (Figure GQ):; 1. Press the OK button () to clear alert (Figure GQ). 2. Replace the battery before the next infusion. See Replacing the Batterysection on pages 81 to 85 for detailed instructions.; Not during an Infusion (Figure GR):; 1. A battery symbol will appear in the top right corner (Figure GR). 2. Replace the battery before next infusion. See Replacing the Batterysection on pages 81 to 85 for detailed instructions on how to replace the pump battery.

Replace Now (Battery Dead)

If the Replace Now Alarm occurs, the battery is dead. Follow the steps below.

Figure GS

What is happening?

You will see a notification (Figure GS) on screen.

What does it mean?

The battery is dead and must be replaced right away.
Note:The pump will not work if the battery is dead.

What to do?

The screen will show a notification (Figure GS):

1. Before setting up or starting an infusion, replace the battery.
  See Replacing the Batterysection on pages 81 to 85 for detailed instructions on how to replace the battery.

Note:The alarms have no intentional delays and are raised as soon as the safety system detects the issue.

Note:The pump's firmware keeps the safety system under constant control, and an Error 2 alarm is raised if any issue is detected.

Note:The LED is used only when it is not possible to show the error on the display. The fact that the LED is not used in other alarms does not necessarily mean that they are of a lower priority.

Troubleshooting: If Your Infusion Line Did Not Prime

Follow the steps below if your infusion line did not prime correctly:

Wake up the pump (if needed) and then repeat the priming procedure. To do this, go to the menu and select Repeat Prime (Figure GT). When priming is complete, continue the procedure by skipping to Step 4.8.

Figure GT

If no liquid drops came out of the site connector end after priming two times, select Endon the Menu screen and throw away the infusion line in a sharps container. Then connect a new Infusion Line and start the priming process again beginning with Step 4.1 on page 33.
See the Disposalsection on page 73 for information on how to safely throw away ONAPGO.

Symbols Used on the ONAPGO Pump

Caution:Consult accompanying documents for important safety-related information.

CF Applied Part, refer to Technical Manual for more information.

Caution:Consult Instructions for Use.

Do not use in or next to a Magnetic Resonance Imaging (MRI) medical device.

Ingress Protection (IP) rating.
Keep pump dry. If wet, wipe off with a dry cloth. The pump must not be immersed in water and must not be used while showering, swimming, or in a sauna.

Prescription device.

Only use the pump with a CR123A battery.

Technical characteristics of the Pump

Dimensions and weight
Dimensions | 81 × 49 × 31 mm
Dimensions with holder attached | 149 × 49 × 31 mm
Weight | 127g
Technical data
Power Supply | CR 123A 3V lithium battery
Battery life | Approximately 90 infusions
Display | Color OLED 96×64 pixels
Ingress protection | IP 42
Buzzer sound pressure level | 53 dBA +/- 5 dBA
Data retention | The value settings and counters are retained even without the battery.
Maximum service life | Two years from date of purchase.
Infusion Data
Note: The information below describes what the pump can do, but it may not be the same as your prescription.
Administrable volume | Max. 20 ml
Infusion flow rate range | 1.0 – 8.0 mg/h (drug concentration is 98 mg/20 mL (4.9 mg/ml))
Flow rate programming increment | 0.1 mg/h
Shot volume | 20 μl
Extra dose (bolus dose) amount | 0.5 - 4.0 mg. May also be set to 0 mg
Bolus dose amount programming increment | 0.1 mg
Maximum number of extra dose (bolus doses) per day | 0-5
Bolus doses per infusion programming increment | 1
Infusion Time Setting | 1 - 24 h
Maximum infusion time programming increment | 1h
Minimum interval between extra doses (bolus doses) | 3 h
Bolus dose interval programming increment | 30 minutes
Bolus dose flow rate | Max. 163 mL/hr
Bolus dose accuracy | Low dose 0.5 to 1.0 mg +/- 25% High dose 1.5 to 4.0 mg +/- 15%
Flow rate accuracy | Low flow rate 1.0 to 3.5 mg/hr: +/- 15% High flow rate 4.0 to 8.0 mg/hr: +/- 10%
Maximum difference in height between pump and infusion site | 50 cm
Priming volume | Fixed 1 ml (first delivery), 0.6 ml (second delivery)
Flow rate during priming | 163 ml/h
Occlusion pressure levels | 2.5 +/- 1.5 bar (36 +/- 22 psi)
Maximum occlusion detection time (hh:mm) | at a flow rate of 1mg/h: 4h 50m at a flow rate of 8mg/h: 32m
Post-occlusion bolus (ml) | 0.85ml
Factory Settings
Infusion flow rate | 1.0 mg/h
Maximum infusion time | 1 h
Bolus dose amount | 0.0 mg
Minimum interval between bolus doses | 3 h
Maximum number of bolus doses per infusion | 0
Environmental Conditions for Use
Temperature | +5 – +40 °C (+41 – +104°F)
Relative humidity | 15 – 68%
Pressure | 0.7 – 1.06 bar (10 – 15 psi)
Environmental Conditions for Storage
Temperature | -25 – +70 °C (-13 – +158°F)
Relative humidity | Max 68%
Pressure | 0.5 – 1.06 bar (7 – 15 psi)

Electromagnetic Compatibility

This section prescribes the correct environments for use in accordance with the declared regulations on electromagnetic compatibility.

Reference standards

The electromagnetic compatibility tests were carried out in accordance with the following standards:

- IEC 60601-2-24:2012 (medical electrical equipment)
- IEC 60601-1-2:2014 (medical electrical equipment)

Electromagnetic emissions

The manufacturer's declarations and requirements are set out below:

Emission test | Conformity | Indications regarding electromagnetic environment
RF emissions CISPR 11 | Group 1 | The pump uses radio frequency only for its internal operation. As a consequence, its RF emissions are very low and would thus not be expected to cause any interference to electronic devices in the vicinity.
RF emissions CISPR 11 | Class B | The pump can be used in all environments, including domestic environments that are directly connected to a low-voltage public mains power network.

Electromagnetic Immunity

The manufacturer's declarations and requirements are set out below:

Immunity test | Test level | Conformity level | Indications regarding electromagnetic environment.
Electrostatic discharge (ESD) IEC 61000-4-2 | 15 kV air 8 kV contact | 15 kV air 8 kV contact | The pump must be used in an environment with wood, concrete or ceramic flooring. Where floors are covered with synthetic material, the relative humidity should be at least 30%.
Magnetic fields | 30 A/m 50 and 60 Hz | 30 A/m 50 and 60 Hz | The pump must be used in an environment with wood, concrete or ceramic flooring. Where floors are covered with synthetic material, the relative humidity should be at least 30%.
Radiated immunity | 80-2700 MHz AM 80% 1 KHz | 10 V/m | The pump may be subject to interference in the vicinity of devices marked with the following symbol:; WARNING! Underdose or overdose due to abnormal pump operation. If the pump is used in the vicinity of other devices, it should be kept under observation in order to verify that no alarms are shown and that the infusion proceeds normally, delivering the drug in the expected time. If in doubt, do not use the device.
IEC 61000-4-3 | 380-390 MHz 18Hz PM 50% | 27 V/m | The pump may be subject to interference in the vicinity of devices marked with the following symbol:; WARNING! Underdose or overdose due to abnormal pump operation. If the pump is used in the vicinity of other devices, it should be kept under observation in order to verify that no alarms are shown and that the infusion proceeds normally, delivering the drug in the expected time. If in doubt, do not use the device.
IEC 61000-4-3 | 430-470 MHz 18Hz PM 50% | 28 V/m | The pump may be subject to interference in the vicinity of devices marked with the following symbol:; WARNING! Underdose or overdose due to abnormal pump operation. If the pump is used in the vicinity of other devices, it should be kept under observation in order to verify that no alarms are shown and that the infusion proceeds normally, delivering the drug in the expected time. If in doubt, do not use the device.
IEC 61000-4-3 | 704-787 MHz 217Hz PM 50% | 9 V/m | The pump may be subject to interference in the vicinity of devices marked with the following symbol:; WARNING! Underdose or overdose due to abnormal pump operation. If the pump is used in the vicinity of other devices, it should be kept under observation in order to verify that no alarms are shown and that the infusion proceeds normally, delivering the drug in the expected time. If in doubt, do not use the device.
IEC 61000-4-3 | 800-960 MHz 18Hz PM 50% | 28 V/m | The pump may be subject to interference in the vicinity of devices marked with the following symbol:; WARNING! Underdose or overdose due to abnormal pump operation. If the pump is used in the vicinity of other devices, it should be kept under observation in order to verify that no alarms are shown and that the infusion proceeds normally, delivering the drug in the expected time. If in doubt, do not use the device.
IEC 61000-4-3 | 1700-1990 MHz 217Hz PM 50% | 28 V/m | The pump may be subject to interference in the vicinity of devices marked with the following symbol:; WARNING! Underdose or overdose due to abnormal pump operation. If the pump is used in the vicinity of other devices, it should be kept under observation in order to verify that no alarms are shown and that the infusion proceeds normally, delivering the drug in the expected time. If in doubt, do not use the device.
IEC 61000-4-3 | 2400-2570 MHz 217Hz PM 50% | 28 V/m | The pump may be subject to interference in the vicinity of devices marked with the following symbol:; WARNING! Underdose or overdose due to abnormal pump operation. If the pump is used in the vicinity of other devices, it should be kept under observation in order to verify that no alarms are shown and that the infusion proceeds normally, delivering the drug in the expected time. If in doubt, do not use the device.
IEC 61000-4-3 | 5100-5800 MHz 217Hz PM 50% | 9 V/m | The pump may be subject to interference in the vicinity of devices marked with the following symbol:; WARNING! Underdose or overdose due to abnormal pump operation. If the pump is used in the vicinity of other devices, it should be kept under observation in order to verify that no alarms are shown and that the infusion proceeds normally, delivering the drug in the expected time. If in doubt, do not use the device.

Recommended separation distances from radio frequency devices

Portable radio frequency communication devices (including external antennas and their cables) may interfere with the pump if they are too close to it. These include mobile and cordless phones, LAN routers and intercom systems for children.

To avoid electromagnetic interference, use the pump at a distance at least 30 cm from such devices.

Tests of Accuracy

The accuracy of pump delivery has been evaluated based on tests carried out during an infusion in accordance with the following standards:

- IEC 60601-2-24:2012 (medical electrical equipment)

Note:Pump and drug cartridge have only been tested with Cleo90 infusion set which is recommended for use. Alternative accessories and extensions may cause inaccuracies in flow rate.

The total administrable volume of the drug is a maximum of 20 mL, and the drug concentration is 98 mg/20 mL (4.9 mg/mL). The flow rate programming increment is 0.5 mg per hr. The maximum infusion programming time is in increment of one hour. The accuracy of the pump was tested for a flow rate between 1.0 mg and 8.0 mg per hour. (See the Prescribing Information for recommended dosage). The flow rate stabilizes within minutes from initiation of the infusion, remains stable and delivers accurately for the duration of infusion as described in the technical specifications provided.

Limited Warranty

The pump is covered by a manufacturer's warranty for two (2) years. After this period, the manufacturer shall not be responsible for any repairs.

The manufacturer shall not be liable for damage to persons or property after a pump lifetime of two (2) years.

Contact & Support

For help and additional information on the pump or system, contact Customer Support at 1-833-3ONAPGO (1-833-366-2746).

Manufactured for:
MDD US Operations, LLC, a
subsidiary of Supernus
Pharmaceuticals, Inc.
Rockville, MD 20850

MDD US Operations, LLC is the exclusive licensee and distributor of ONAPGO in the United States and Its territories.

©2025. ONAPGO is a registered trademark of BRITUSWIP LTD.

Version 14

This Instructions for Use has been approved by the U.S. Food and Drug Administration.

Revised: 06/2025

Healthcare Provider INSTRUCTIONS FOR USE ONAPGO™ (on-AP-goh)

This Instructions for Use contains information for healthcare providers on how to program the infusion pump to administer ONAPGO (apomorphine hydrochloride).

Please see the Important Safety Information, full Prescribing Information, and Patient Informationfor ONAPGO.

MDD US Operations, LLC

Table of Contents
Table of Contents | 2
ONAPGO Infusion System | 3
Indication for Use | 3
Introduction to the Infusion System | 3
Pump Warnings and Precautions | 4
Pump Kit | 5
Pump Diagram | 5
Pump Screen Icons | 7
Programming the ONAPGO Pump | 8
Settings Overview | 8
Step 1: Access Pump Settings | 9
Step 2: Enter Password | 10
Step 3: Program Pump Settings | 11
Symbols Used on the ONAPGO Pump | 20
Limited Warranty | 21
Contact & Support | 21

ONAPGO Infusion System

Indication for Use

The ONAPGO Infusion Pump is for the subcutaneous infusion of ONAPGO (apomorphine hydrochloride). ONAPGO is indicated for the treatment of motor fluctuations in adults with advanced Parkinson's disease (PD).

It must be used only by individuals who have received instruction and training on its operations and on the correct, safe procedures. If patients are unable to give treatment independently, they must be given assistance and supervision.

Only the accessories supplied by CANÈ S.p.A. (plastic cartridge holder and supplies provided in the infusion pump kit) may be used in conjunction with this pump. The pump must be programmed by an adequately trained healthcare provider and/or a Supernus Pharmaceuticals/MDD US Operations Clinical Nurse Navigator (clinical nurse navigator).

Introduction to the Infusion System

Below are the common terms used throughout this Instructions for Use.

- Pump:controls the rate and amount of ONAPGO delivered to the body. It is programmed with the patient's prescription and displays the status of medicine delivery.
- Priming:refers to the task of removing all air from the Infusion Line (fluid pathway) before the infusion line is connected to the body.
- Flow Rate:the constant flow of ONAPGO given to the body over an extended period of time. The flow rate is expressed as milligrams per hour (mg/hr).
- Infusion Time:the total time that ONAPGO is infused per day.
- Extra Dose (+ Dose):a boost of ONAPGO (bolus dose) given over a short period of time in addition to the prescribed flow rate.
- Extra Dose (+ Dose) Lock:the amount of time before another extra dose can be given.
- Pump Settings:the patient's prescribed Flow Rate, Maximum Infusing Time Per Day, +Dose Quantity, +Dose Volume, and +Dose Lock. These settings can only be changed by a Healthcare Provider and/or Supernus Clinical Nurse Navigator.

Pump Warnings and Precautions

WARNINGS:

- Do notgive a patient a pump without checking the prescription. Always check that the pump Settings match the patient's prescription before giving the pump to a patient.
- Do notstart an infusion without confirming the patient's prescription. If the pump settings do not match the prescription, do not allow the patient to use the pump. Reprogram the pump to match the prescription.
- Do notgive a patient more than 98 mg of ONAPGO over a 24-hour period.
- Do notdisclose the pump's security codes or other information to the patient. It would allow them access to the programming functions.
- Use ONAPGO drug cartridges with the ONAPGO pump only.

PRECAUTIONS:

- Do notuse sharp objects to press the pump buttons. Only use your fingertips.
- Do notuse a damaged pump. If you have any concerns about the correct functioning of the pump, and/or how to respond to an error contact your customer support representative.

Pump Kit (Figure A)

Pump Diagram (Figures B, C, and D)

Figure B

Figure D

Figure C

All buttons will respond with a single press. If the screen is dark, press the UP ARROW () to wake up the screen.

Item | Pump Feature | Description
a | Cartridge Connection | Area where assembled glass drug cartridge and plastic cartridge holder is attached to the pump.
b | Pump Pusher | Pushes ONAPGO from the glass drug cartridge into the Infusion Line.
c | Neck Lanyard Clips | Slots to clip on the lanyard.
d | LED | Lights up when an error cannot be displayed on the screen.
e | Screen | Where messages and menus appear.
f |  | +DOSE button gives an extra dose (if prescribed).
g |  | BACK button allows you to return to a previous screen, menu, or cancel an action.
h |  | MENU button allows you to access the menus.
i |  | OK button allows you to confirm menu selections or go on to the next value.
j |  | UP and DOWN ARROW buttons allow you to scroll through menus.
k | Battery Door | Door to access the battery.

Pump Screen Icons

The following table shows Icons that appear on the Pump screen.

Icon | Name | Description
 | Back Arrow | The back arrow is shown when checking the pump settings. This icon is used to show that pressing the BACK button will return to a previous screen (Item 'g' in Figure B).
 | Caution | Caution is shown when an error or alarm is occurring.
 | Check Mark | A check mark is shown when the Pump successfully completes a task.
 | Droplet | A blinking droplet is shown on the Infusing Screen when an infusion is on.
 | Dead Battery | The dead battery is shown when the Pump battery is dead and must be replaced.
 | Low Battery | The low battery is shown when the pump battery is low and should be replaced before the next infusion.
 | OK Arrow | The OK arow is shown when checking the pump settings. This icon is used to show that pressing the OK button will confirm a selection or go on to the next value (Item 'i' in Figure B).
 | Padlock | Padlock is shown when the +Dose (extra dose) is not available.
 | Pause | Pause is shown when the infusion is paused.
 | +Dose (Extra Dose) | A +symbol refers to the extra dose (+Dose) function.

Programming the ONAPGO Pump

The pump cannot be programmed while infusing.

The pump settings should be programmed according to the patient's prescription before they receive the pump.

Settings Overview

When programming the pump, a flashing value is one that you may edit. The table below describes the default pump settings and range of values to which the pump can be programmed. See the Prescribing Information for the recommended dosage regimen, including the recommended flow rate (i.e., 1 mg/hr to 6 mg/hr), infusion time (i.e., generally over 16 waking hours), and extra doses (i.e., no more than 3 per day).

Icon | Default Pump Setting | Range of Values | Increments | Refer To
Time | Factory setting | 12:00 AM - 11:59 PM | N/A | Step 3.1 (page 11)
Date | Factory setting | mm/dd/yy | N/A | Step 3.2 (page 12)
Flow Rate | 1 mg/hr | 1 - 8 mg/hr | 0.5 mg/hr | Step 3.3 (page 13)
Infusion Time | 1 hr | 1 - 24 hr | 1 hr | Step 3.4 (page 14)
+Doses/Day (Extra Doses/Day) | 0 (No Bolus) | 0 - 5 | 1 | Step 3.5 (page 15)
+Dose | 0 mg | 0.5 - 4 mg | 0.5 mg | Step 3.6 (page 16)
+Dose Lock | 3 hr | 0 - 24 hr | 30 min | Step 3.7 (page 17)

Step 1: Access Pump Settings

Step 1.1
If the pump screen is asleep, press the UP ARROW () to wake it up (Figure E).
Note:Do this anytime you need to wake up the pump.

Figure E

When the pump wakes up, the screen will say Infusion Off (Figure F).

Figure F

Step 1.2
Press and hold the OK button (). While continuing to hold, press and hold the UP ARROW at the same time (Figure G), until a password input screen appears (Figure H).
You will hear a series of beeps when holding both the UP ARROW () and OK button ().

Figure G

Keep holding both buttons until the password screen appears.
You will then see the password screen (Figure H).

Figure H

Step 2: Enter Password

Important Information:
Do notdisclose the pump's security codes or other information to the patient. It would allow them access to the programming functions.

Step 2.1
Locate the 4-digit password on the back of the pump (Figure I).
The password is the 4 numbers following 'AJ'. In the example provided (Figure I), the 4-digit password would be 0001.

HCP password on back of pump
Figure I

Step 2.2
Use the UP AND DOWN ARROWS () to change the values on the Password screen (Figure J). Flashing values indicate that they are currently being edited. When the selected number matches the pump password, press the OK button () to proceed to the next number. Repeat this process for all 4 numbers.

Figure J

When the correct password has been entered, press the OK button () to proceed to the Time screen (Figure K).
Note:If incorrect password is entered, the pump will go to the Infusion Off screen. Repeat steps 2.1 and 2.2 (above) with the correct password.

Figure K

Step 3: Program Pump Settings

If this is the first time the pump will be programmed, the existing values will reflect the default factory settings (Page 8).

For any subsequent programming, the values will reflect the previously programmed patient prescription.

The settings will need to be changed to match the time, date, and patient's prescription.

Step 3.1
Use the UP and DOWN ARROWS () to change the hour. As the hour is adjusted, the AM and PM will also change. When the hour and AM/PM are correct, press the OK button () to change the minutes (Figure L). Use the UP and DOWN ARROWS () to change the minutes.

Figure L

When the Time is correct, press the OK button () to proceed to the Date screen (Figure M) Step 3.2.

Figure M

Step 3.2
Use the UP and DOWN ARROWS () to change the month and press the OK button () to continue to change the day and year (Figure N).

Figure N

When the date is correct, press the OK button () to proceed to the Flow Rate screen (Figure O) Step 3.3.

Figure O

Step 3.3
Use the UP and DOWN ARROWS () to change the flow rate (Figure P).

Figure P

When the flow rate is correct, press the OK button () to proceed to the Infusion Time screen (Figure Q) Step 3.4.

Figure Q

Note:If you are prescribing above the recommended flow rate, a Verify screen will appear (Figure R).
Press the OK button () to proceed or press the BACK button () to edit the flow rate.

Figure R

Step 3.4
Use the UP and DOWN ARROWS () to change the Infusion Time (length of time that infusion will run) (Figure S).

Figure S

When the infusion time is correct, press the OK button () to proceed to the + Doses/Day (extra doses/day) screen (Figure T) Step 3.5.

Figure T

Note:If you are prescribing above the recommended infusion time, a Verify screen will appear (Figure U).
Press the OK button () to proceed or press the BACK button () to edit the infusion time.

Figure U

Step 3.5
Use the UP and DOWN ARROWS () to change the number of allowable +Doses (extra doses) that can be delivered per Day (Figure V).
Note:If no +dose (extra dose) is prescribed, enter '0' for the number of +Doses/Day (extra doses/ day) and press the OK button () to proceed to the +Dose screen (Figure W) Step 3.6. If no +Doses/Day (extra doses/day) are prescribed, the subsequent +Dose and +Dose Lock screen values cannot be changed.

Figure V

When the +Doses/Day (extra doses/ day) number is correct, press the OK button () to proceed to the +Dose screen (Figure W) Step 3.6.

Figure W

Note:If you are prescribing above the recommended +Doses/Day, a Verify screen will appear (Figure X).
Press the OK button () to proceed or press the BACK button () to edit the +Doses/Day (extra doses/day).

Figure X

Step 3.6
Use the UP and DOWN ARROWS () to change the +Dose (Extra Dose) value (mg) (Figure Y).
Note:If no extra doses are prescribed, the +Dose value cannot be changed. Press the OK button () to proceed to the +Dose Lock screen (Figure Z) Step 3.7.

Figure Y

When the +Dose (extra dose) value is correct, press the OK button () to proceed to the +Dose Lock screen (Figure Z) Step 3.7.

Figure Z

Note:If you are prescribing above the recommended extra doses, a Verify screen will appear (Figure AA). Press the OK button () to proceed or press the BACK button () to edit the +Dose (extra dose).

Figure AA

Step 3.7
Use the UP and DOWN ARROWS () to change the + Dose Lock (extra dose lock) time (time patient must wait before another extra dose) (Figure AB).
Note:If no extra doses are prescribed, the + Dose (extra dose) lock time cannot be changed. Press the OK button () to proceed to the Verify Rx screen (Figure AC) Step 3.8.

Figure AB

When the + Dose (extra dose) lock time is correct, press the OK button () to proceed to the Verify Rx screen (Figure AC) Step 3.8.

Figure AC

Step 3.8
When the Verify Rx screen appears (Figure AD), press the DOWN ARROW () to confirm that each pump setting programmed matches the patient's prescription.

Figure AD

Continue pressing the DOWN ARROW () until the Back/OK row is highlighted (Figure AE).

Figure AE

Step 3.9
If the programmed pump settings match the patient's prescription, press the OK button () to save the pump settings (Figure AF).
Note:If any of the programmed pump settings do not match the patient's prescription, use the BACK button () to go back to the setting and adjust accordingly.

Figure AF

When the pump is done saving, the Infusion Off screen will appear (Figure AG).
Note:If the OK button is not pressed and the pump screen falls asleep (goes dark), the programmed pump settings will still be saved.

Figure AG

Symbols Used on the ONAPGO Pump

Caution:Consult accompanying documents for important safety-related information.

CF Applied Part, refer to Technical Manual for more information.

Caution:Consult Instructions for Use.

Do not use in or next to a Magnetic Resonance Imaging (MRI) medical device.

Ingress Protection (IP) rating.
Keep pump dry. If wet, wipe off with a dry cloth. The pump must not be immersed in water and must not be used while showering, swimming, or in a sauna.

Prescription device.

The pump is to only be used with a CR123A battery.

Note:The symbols displayed on the product label are reduced and simplified compared to the specifications in the reference standard CENELEC EN50419.

Limited Warranty

The pump is covered by a manufacturer's warranty for two (2) years. After this period, the manufacturer shall not be responsible for any repairs.

The manufacturer shall not be liable for damage to persons or property after a pump lifetime of two (2) years.

Contact & Support

For help and additional information on the pump or system, contact Customer Support at 1-833-3ONAPGO (1-833-366-2746).

Manufactured for:
MDD US Operations, LLC, a
subsidiary of Supernus Pharmaceuticals, Inc.
Rockville, MD 20850

MDD US Operations, LLC is the exclusive licensee and distributor of ONAPGO in the United States and Its territories.

©2025. ONAPGO is a registered trademark of BRITUSWIP LTD.

Version 8

This Instructions for Use has been approved by the U.S. Food and Drug Administration.

Revised: 06/2025

PRINCIPAL DISPLAY PANEL - 20 mL Cartridge Carton

ONAPGO™
(apomorphine HCl)
injection, for subcutaneous use

NDC 27505-006-05
Rx Only

98 mg/20 mL (4.9 mg/mL)

Single-dose cartridge.
Discard unused portion.

Package contains 5 x 20 mL cartridges